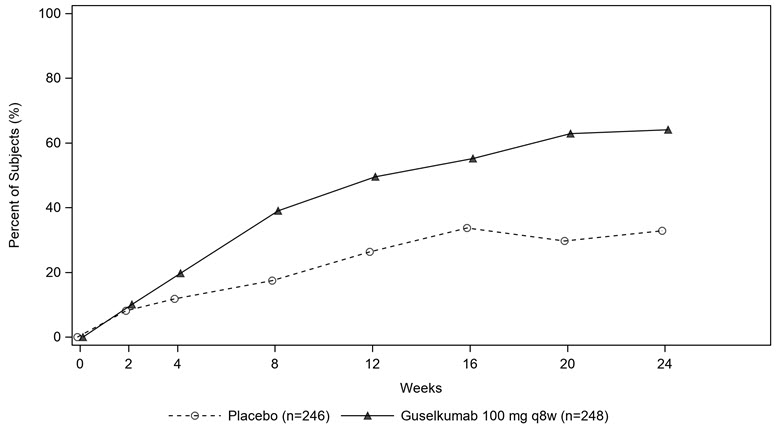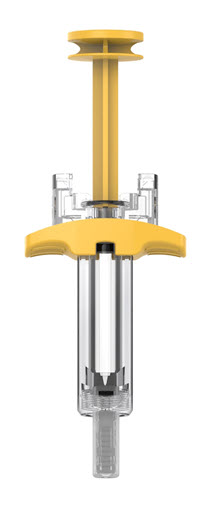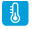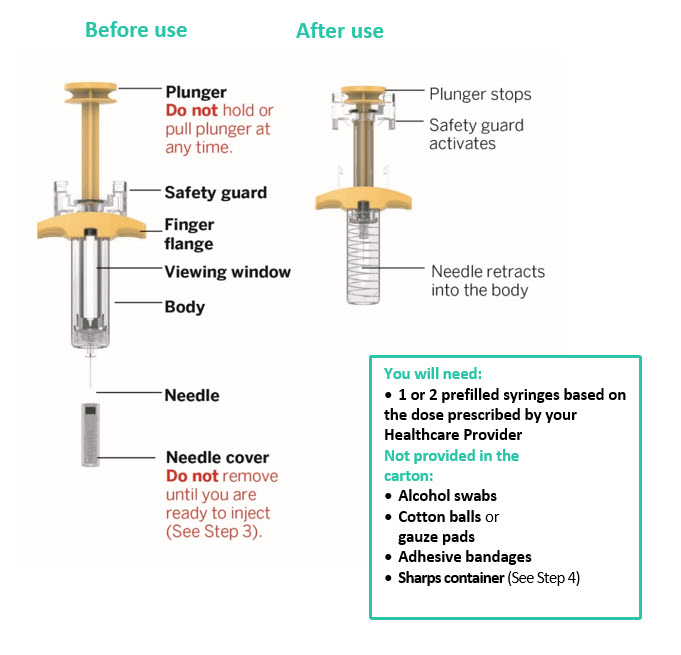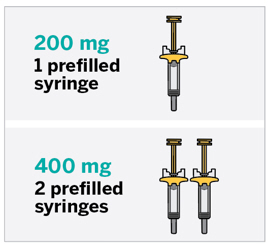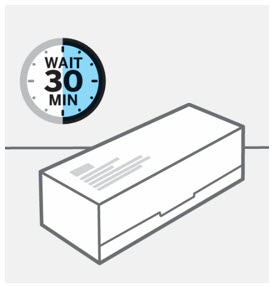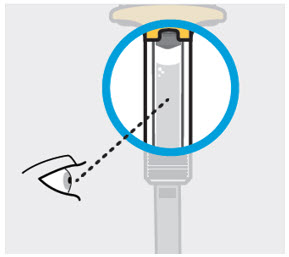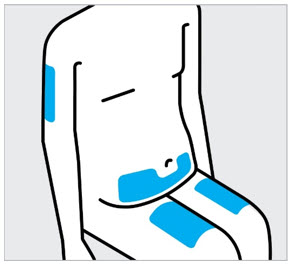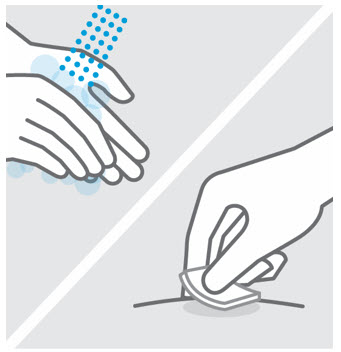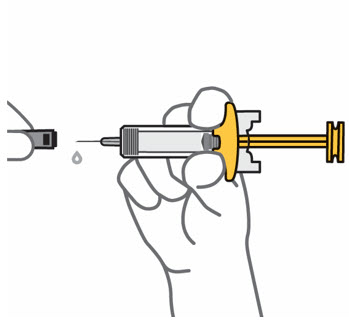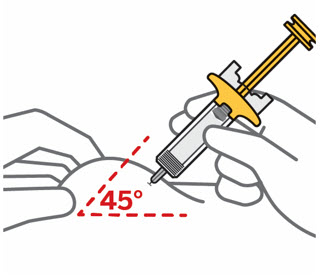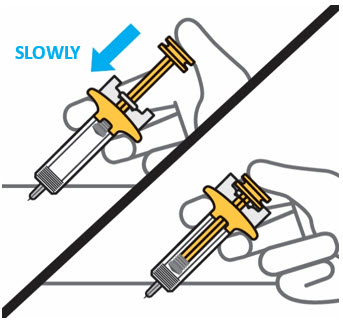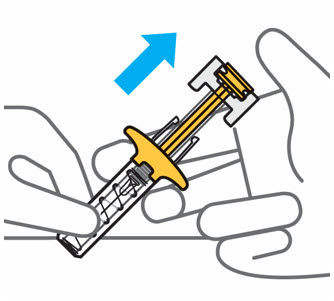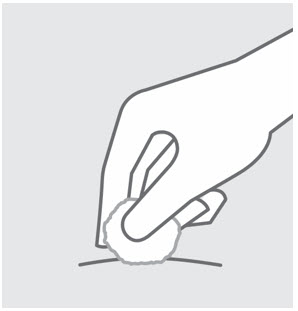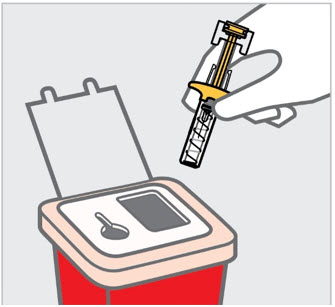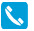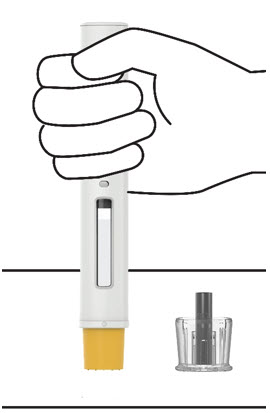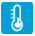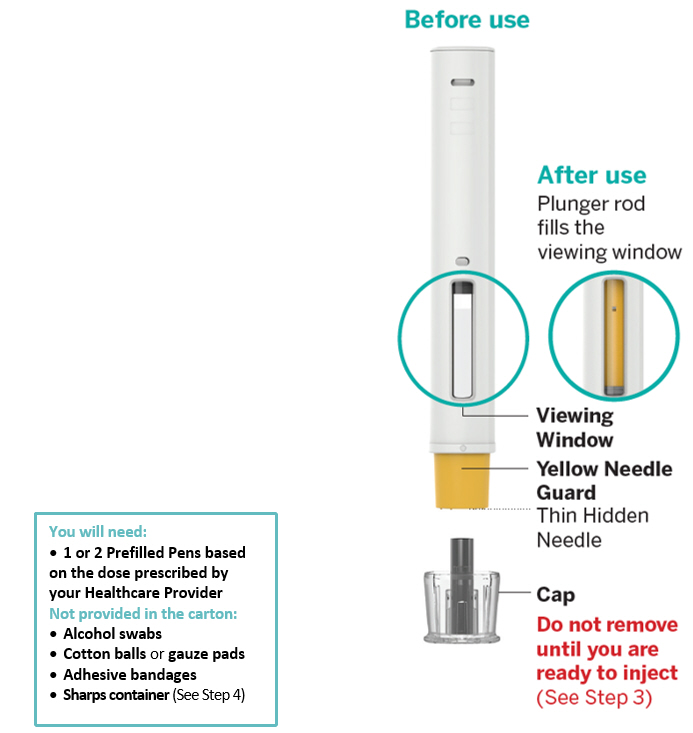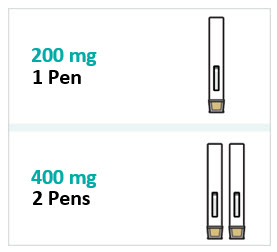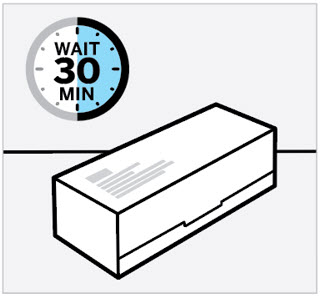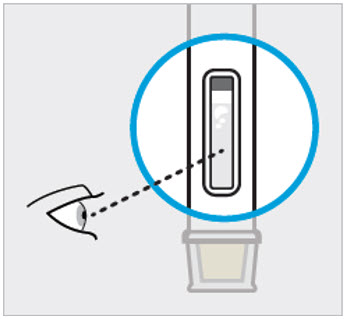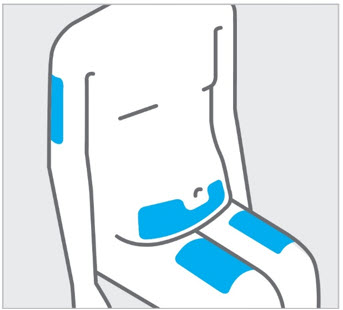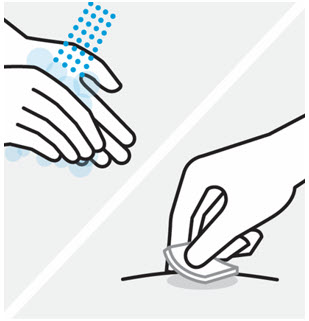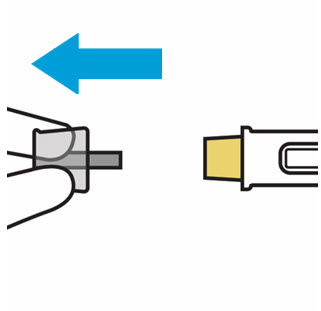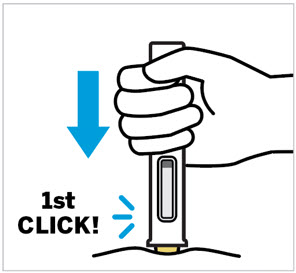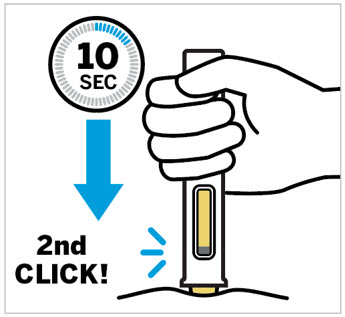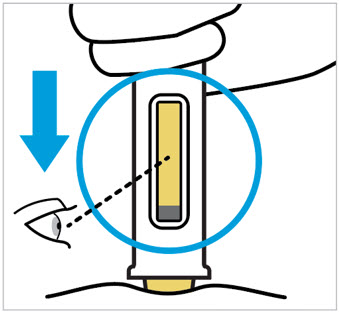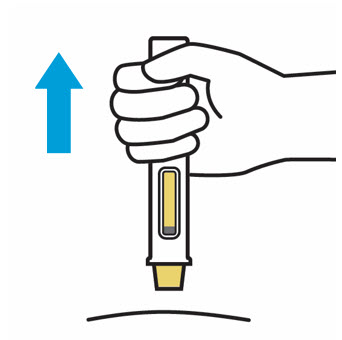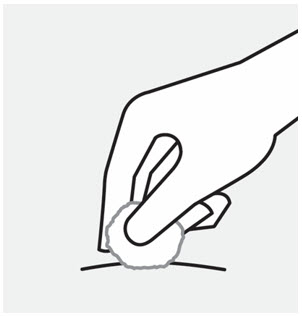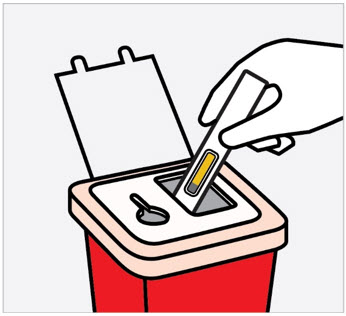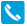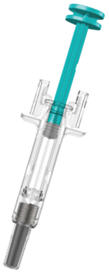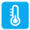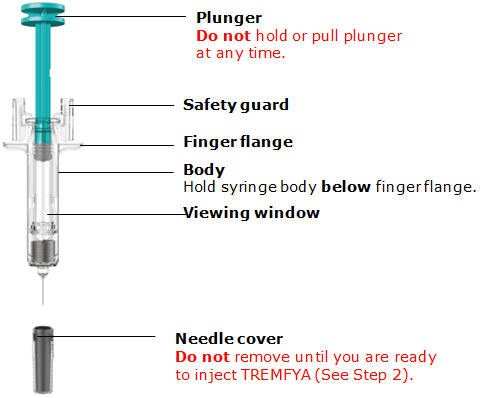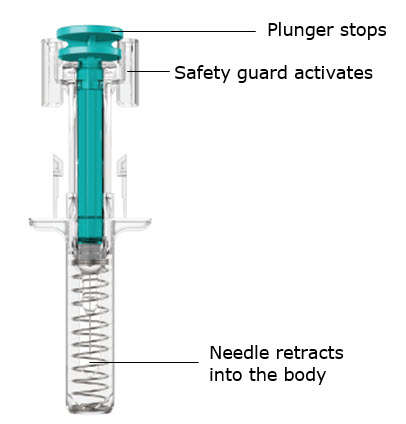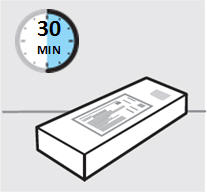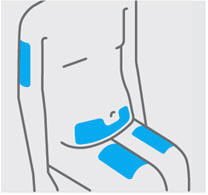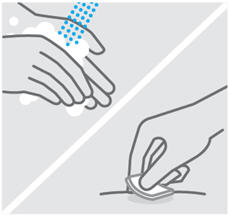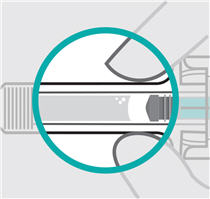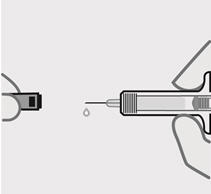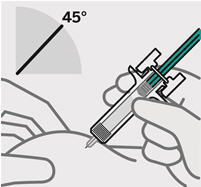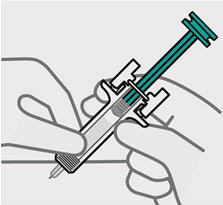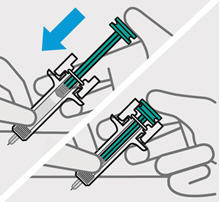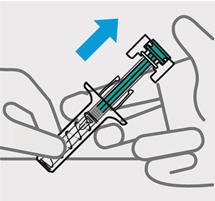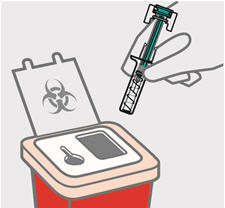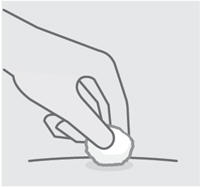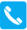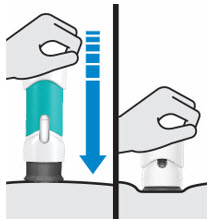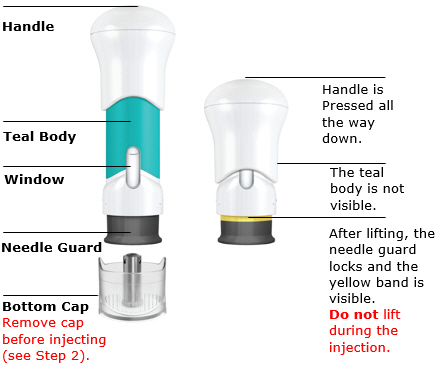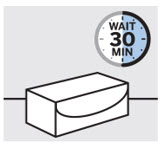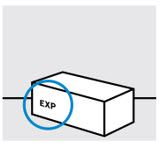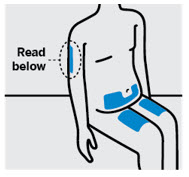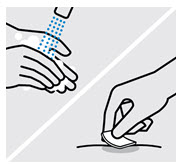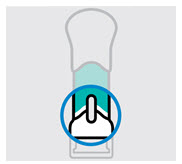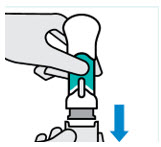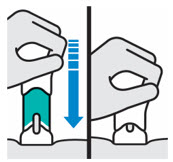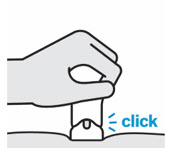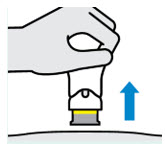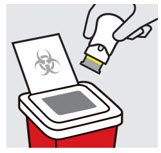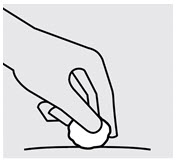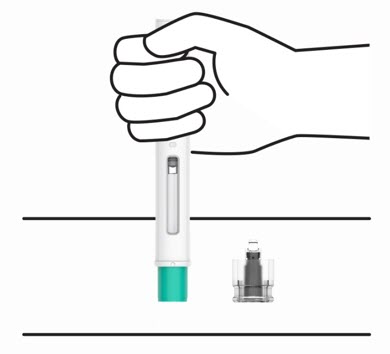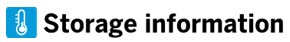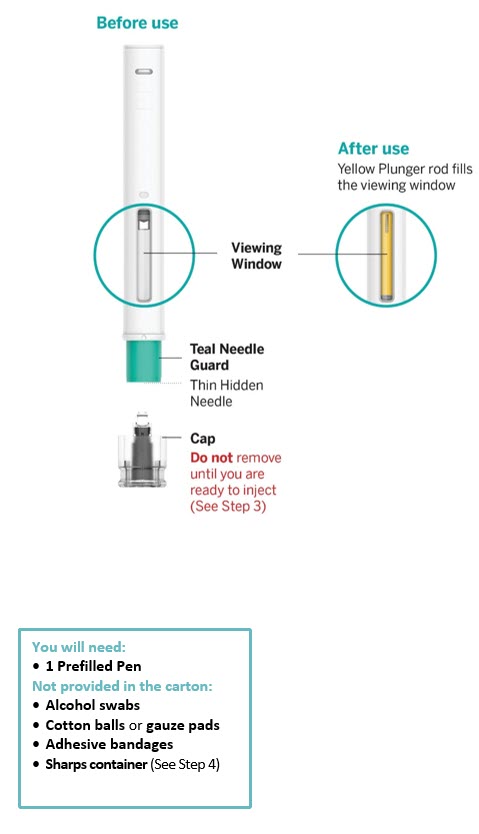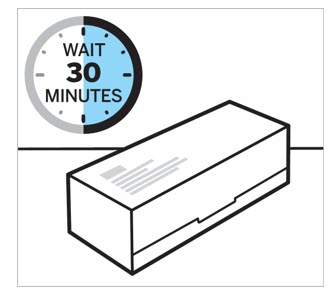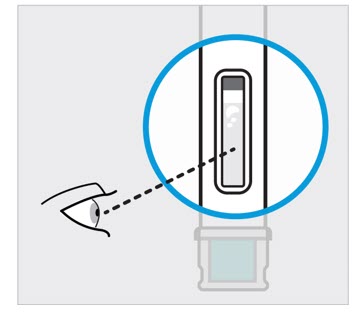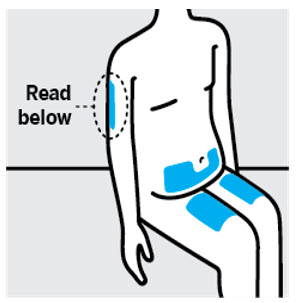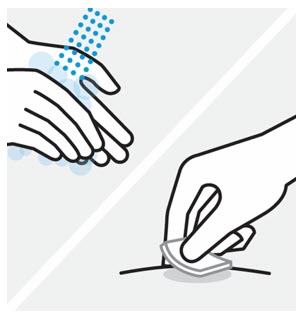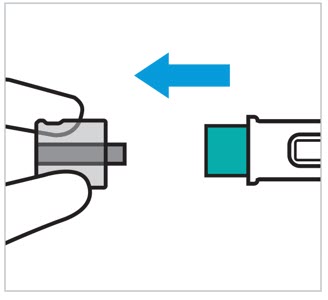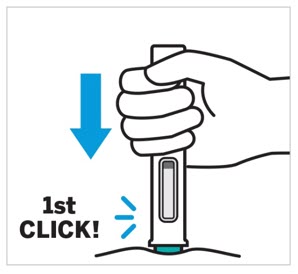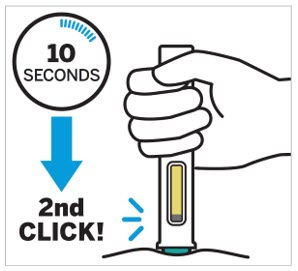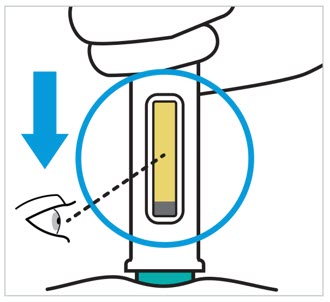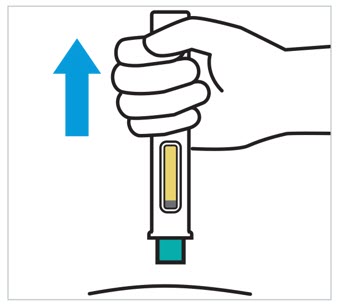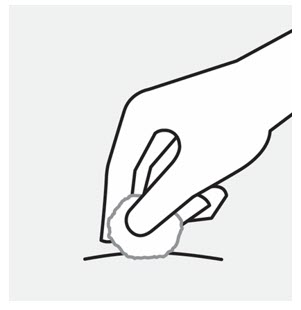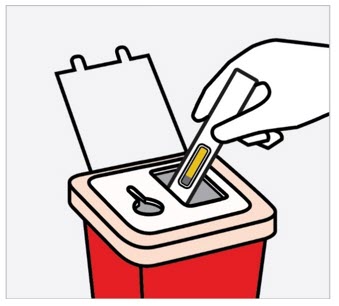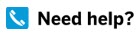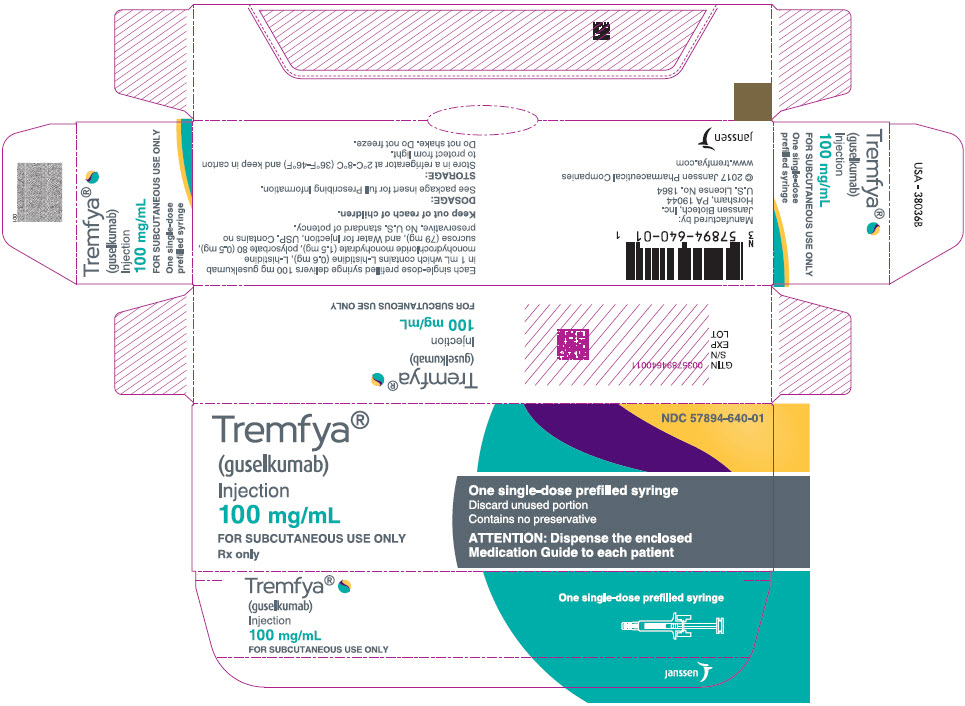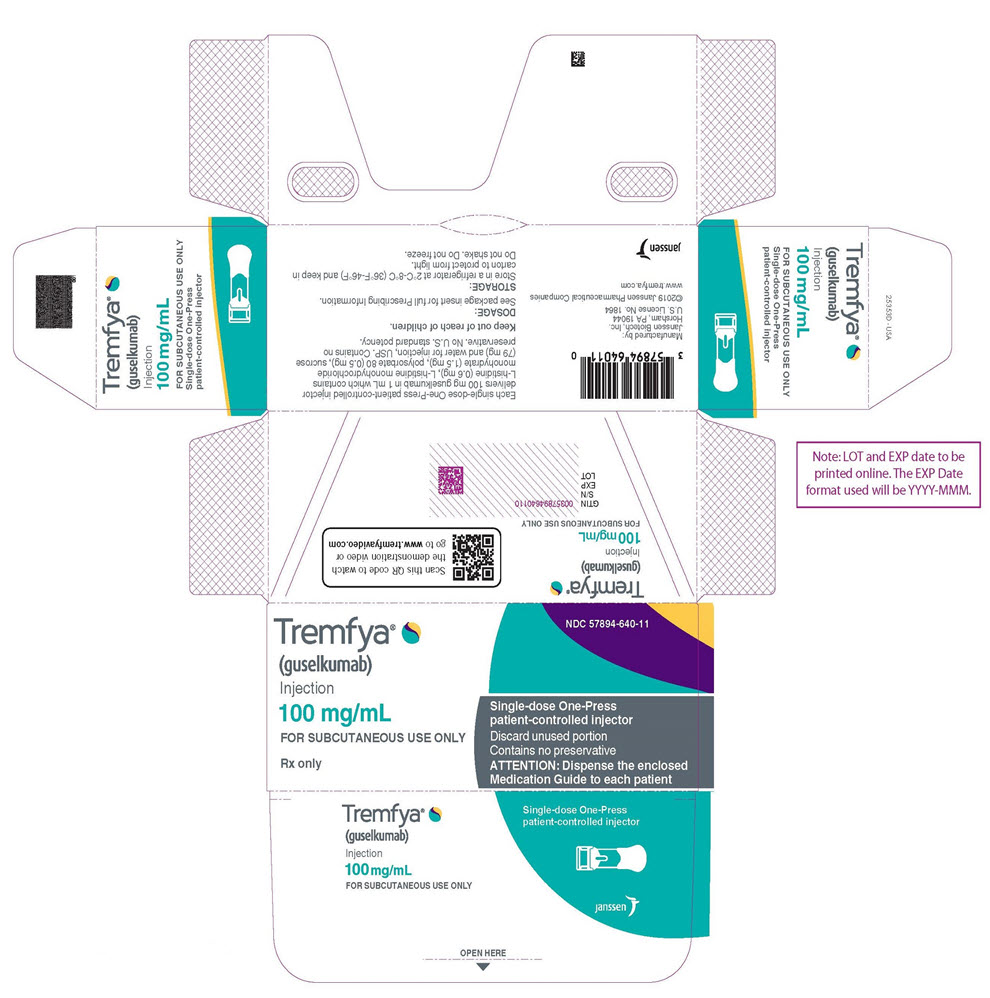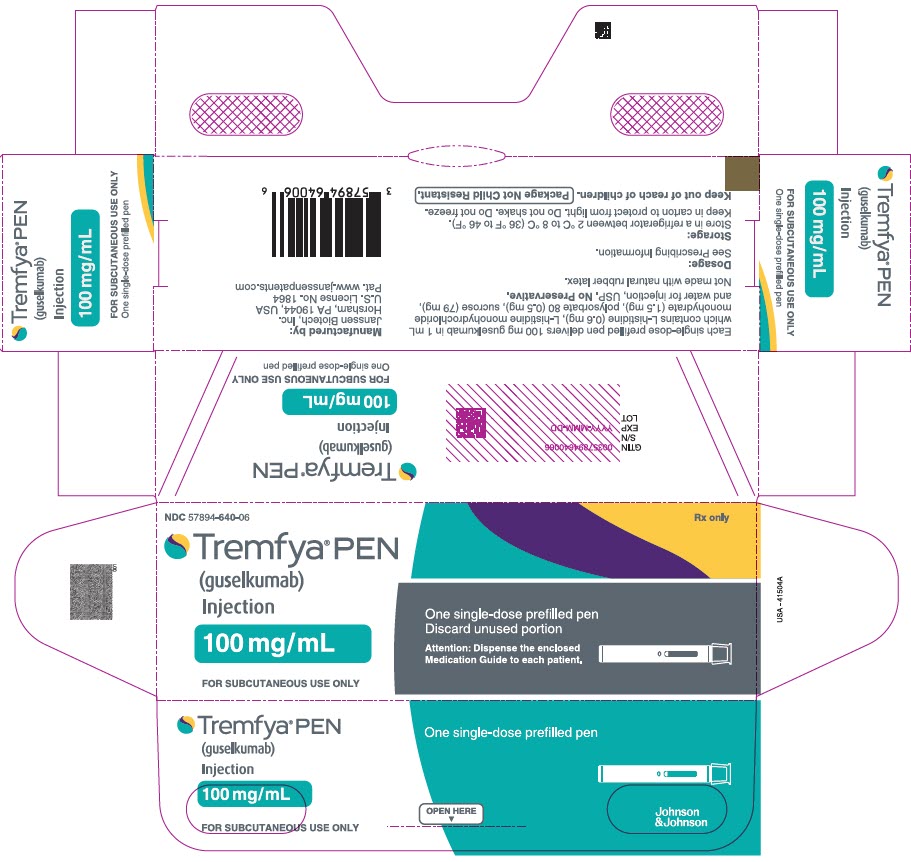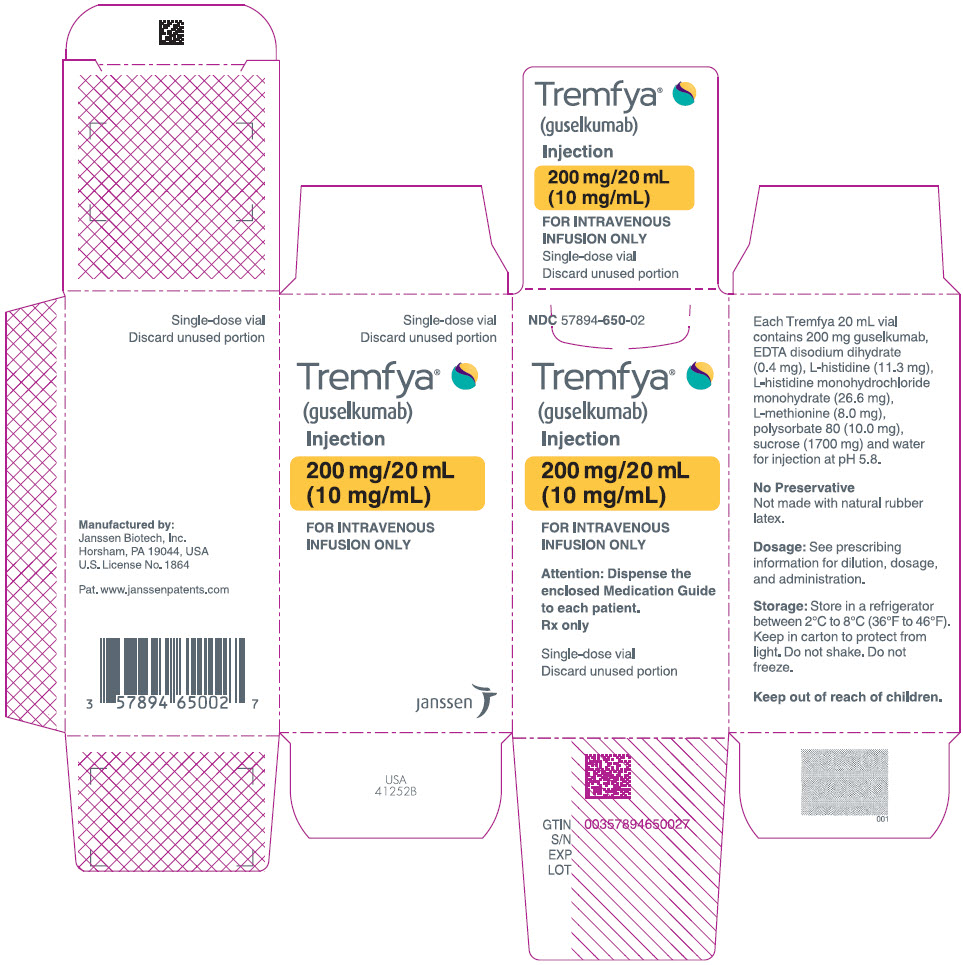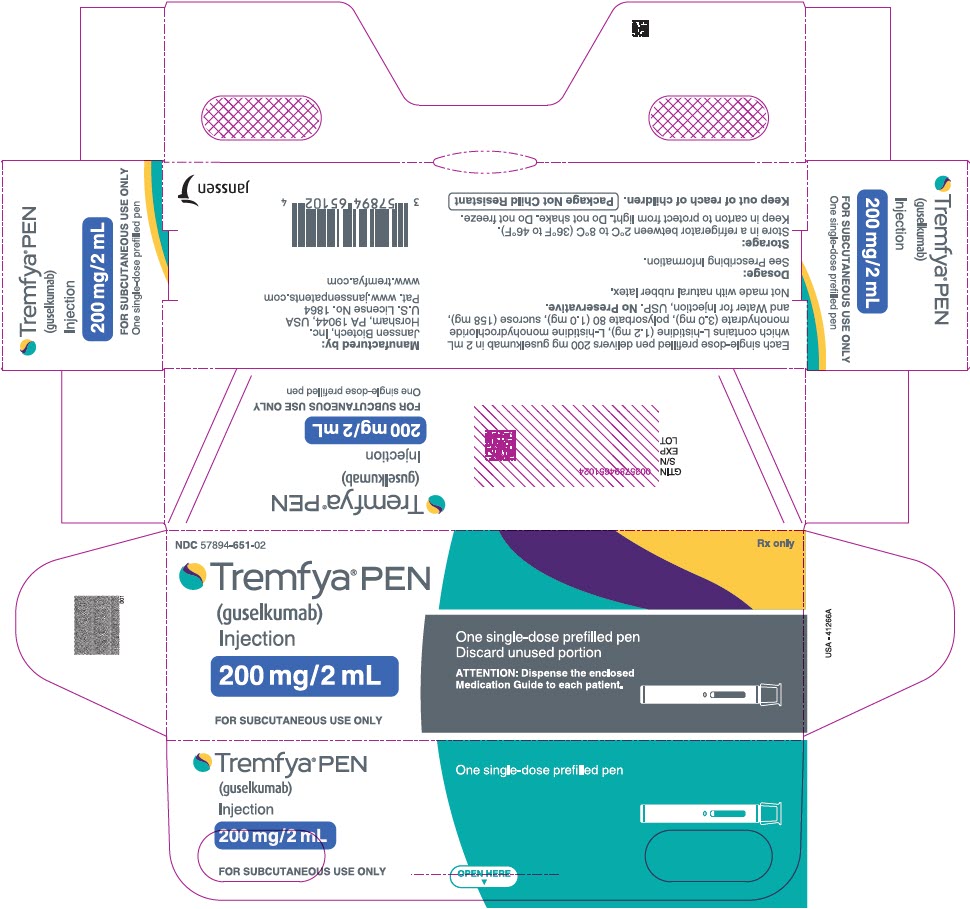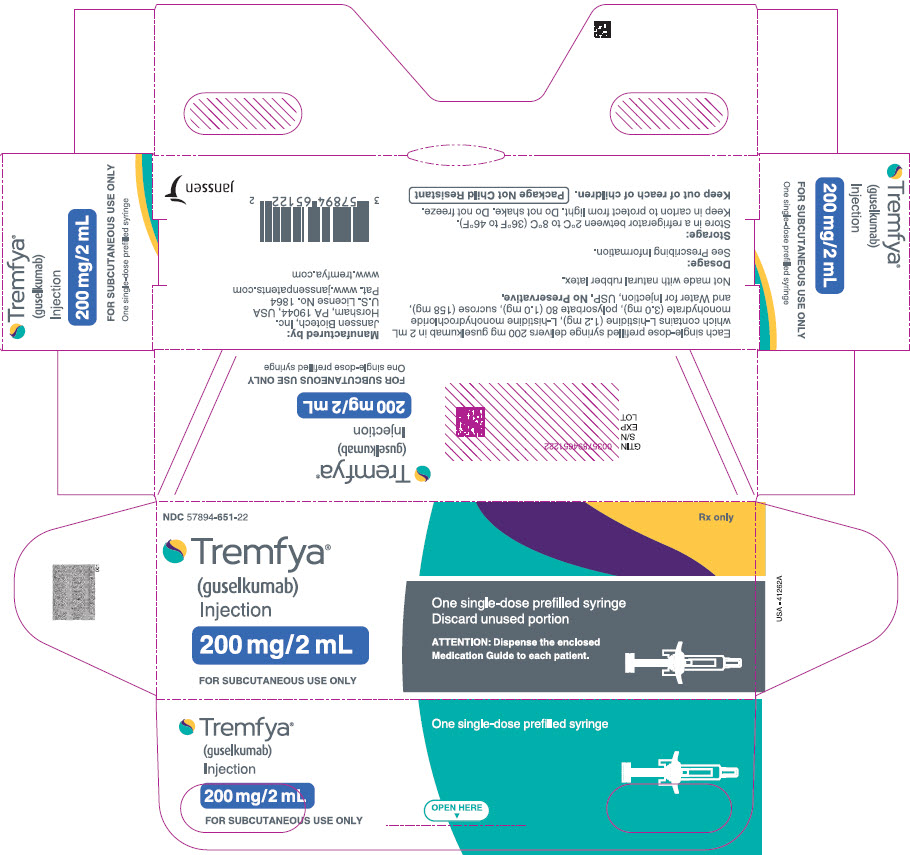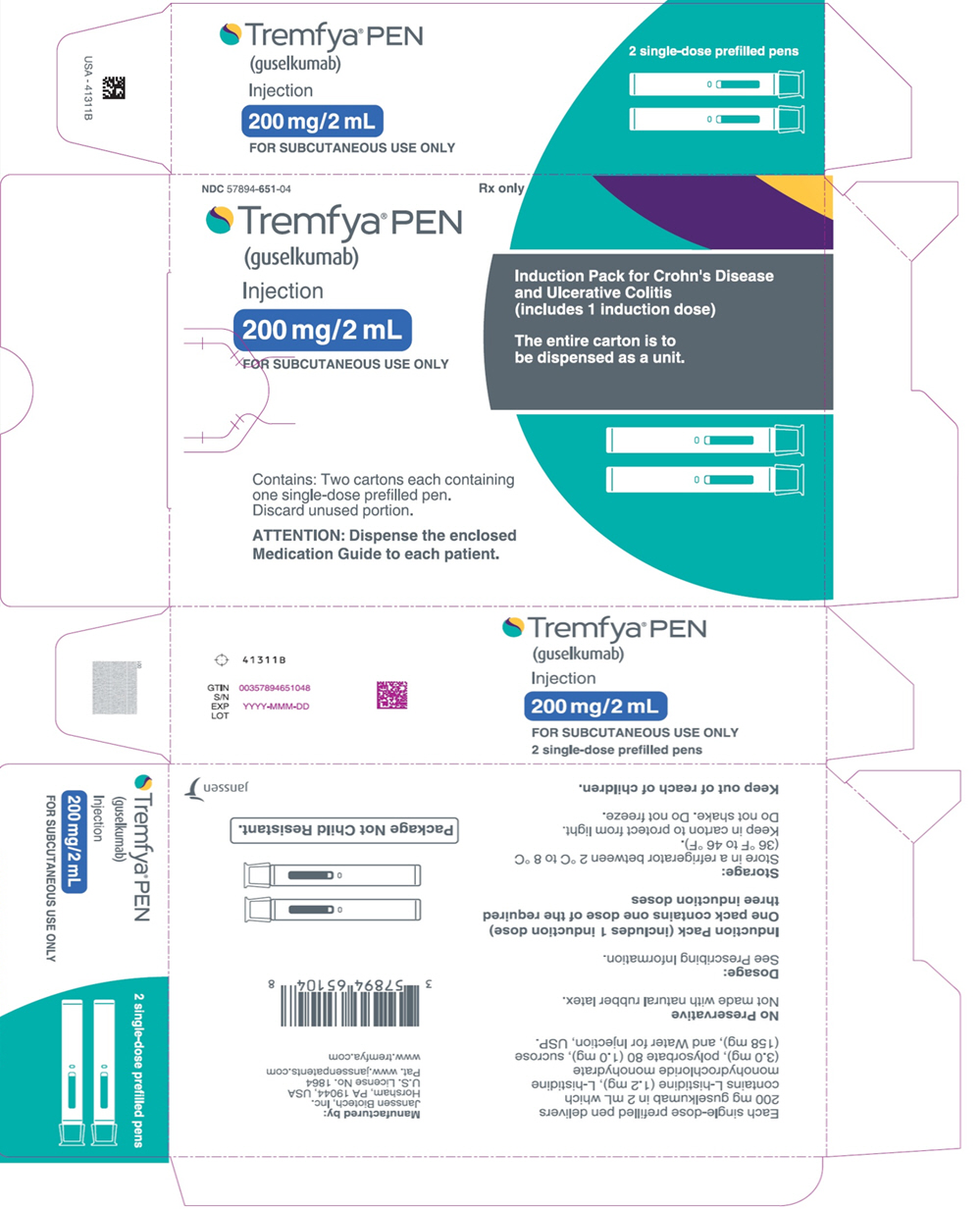 DRUG LABEL: TREMFYA
NDC: 57894-650 | Form: INJECTION
Manufacturer: Janssen Biotech, Inc.
Category: prescription | Type: HUMAN PRESCRIPTION DRUG LABEL
Date: 20250929

ACTIVE INGREDIENTS: GUSELKUMAB 200 mg/20 mL
INACTIVE INGREDIENTS: EDETATE DISODIUM 0.4 mg/20 mL; HISTIDINE 11.3 mg/20 mL; METHIONINE 8 mg/20 mL; POLYSORBATE 80 10 mg/20 mL; SUCROSE 1700 mg/20 mL; WATER

HIGHLIGHTS OF PRESCRIBING INFORMATION

These highlights do not include all the information needed to use TREMFYA safely and effectively. See full prescribing information for TREMFYA.
TREMFYA® (guselkumab) injection, for subcutaneous or intravenous use
Initial U.S. Approval: 2017

RECENT MAJOR CHANGES

Indications and Usage (1.4) | 03/2025
Indications and Usage (1.1, 1.2) | 09/2025
Dosage and Administration (2.1, 2.5, 2.6) | 03/2025
Dosage and Administration (2.2, 2.3, 2.5) | 09/2025
Dosage and Administration (2.4) | 09/2025
Warnings and Precautions (5.3, 5.4) | 03/2025
Warnings and Precautions (5.2, 5.4) | 09/2025

1 INDICATIONS AND USAGE

TREMFYA is an interleukin-23 antagonist indicated for the treatment of:

- adults and pediatric patients 6 years of age and older who also weigh at least 40 kg with moderate-to-severe plaque psoriasis and who are candidates for systemic therapy or phototherapy. (1.1)
- adults and pediatric patients 6 years of age and older who also weigh at least 40 kg with active psoriatic arthritis. (1.2)
- adults with moderately to severely active ulcerative colitis. (1.3)
- adults with moderately to severely active Crohn's disease. (1.4)

2 DOSAGE AND ADMINISTRATION

- For the treatment of ulcerative colitis or Crohn’s disease: Obtain liver enzymes and bilirubin levels prior to initiating treatment with TREMFYA. (2.1, 5.4).
- For the treatment of plaque psoriasis or psoriatic arthritis, if clinically indicated, evaluate liver enzymes and bilirubin at baseline prior to initiating treatment with TREMFYA (2.1, 5.4).
- Complete all age-appropriate vaccinations as recommended by current immunization guidelines prior to treatment initiation. (2.1)

Recommended Dosage

Plaque Psoriasis

Adults

- 100 mg administered by subcutaneous injection at Week 0, Week 4, and every 8 weeks thereafter. (2.2)

Pediatric Patients 6 Years of Age and Older Who Also Weigh at Least 40 kg

- 100 mg administered by subcutaneous injection at Week 0, Week 4, and every 8 weeks thereafter. (2.2)

Psoriatic Arthritis

Adults

- 100 mg administered by subcutaneous injection at Week 0, Week 4, and every 8 weeks thereafter. TREMFYA can be used alone or in combination with a conventional DMARD (e.g., methotrexate). (2.3)

Pediatric Patients 6 Years of Age and Older Who Also Weigh at Least 40 kg

- 100 mg administered by subcutaneous injection at Week 0, Week 4, and every 8 weeks thereafter. TREMFYA may be administered alone or in combination with a conventional disease-modifying antirheumatic drug (e.g., methotrexate). (2.3)

Ulcerative Colitis and Crohn’s Disease

- Induction: 200 mg administered by intravenous infusion over at least one hour at Week 0, Week 4, and Week 8 or 400 mg administered by subcutaneous injection at Week 0, Week 4, and Week 8. (2.4)
- Maintenance: 100 mg administered by subcutaneous injection at Week 16, and every 8 weeks thereafter, or 200 mg administered by subcutaneous injection at Week 12, and every 4 weeks thereafter. Use the lowest effective recommended dosage to maintain therapeutic response. (2.4)

3 DOSAGE FORMS AND STRENGTHS

Subcutaneous Injection (3)

- Injection: 100 mg/mL in a single-dose One-Press patient-controlled injector.
- Injection: 100 mg/mL in a single-dose prefilled pen (TREMFYA PEN).
- Injection: 200 mg/2 mL in a single-dose prefilled pen (TREMFYA PEN).
- Injection: 100 mg/mL in a single-dose prefilled syringe.
- Injection: 200 mg/2 mL (100 mg/mL) in a single-dose prefilled syringe.

Intravenous Infusion (3)

- Injection: 200 mg/20 mL (10 mg/mL) solution in a single-dose vial.

4 CONTRAINDICATIONS

Serious hypersensitivity reactions to guselkumab or to any of the excipients. (4)

5 WARNINGS AND PRECAUTIONS

- Hypersensitivity Reactions: Serious hypersensitivity reactions, including anaphylaxis, may occur. (5.1)
- Infections: TREMFYA may increase the risk of infections. Do not initiate treatment with TREMFYA in patients with clinically important active infection until the infection resolves or is adequately treated. If such an infection develops, discontinue TREMFYA until the infection resolves. (5.2)
- Tuberculosis (TB): Evaluate for TB prior to initiating treatment with TREMFYA. Monitor patients for signs and symptoms of active TB during and after treatment with TREMFYA. (5.3)
- Hepatotoxicity: Drug-induced liver injury has been reported. For the treatment of ulcerative colitis or Crohn’s disease, evaluate liver enzymes and bilirubin levels at baseline, for at least 16 weeks of treatment, and periodically thereafter according to routine patient management. For the treatment of plaque psoriasis or psoriatic arthritis, if clinically indicated, evaluate liver enzymes and bilirubin at baseline, and periodically thereafter according to routine patient management. Interrupt treatment if drug-induced liver injury is suspected, until this diagnosis is excluded. (5.4)
- Immunizations: Avoid use of live vaccines. (5.5)

6 ADVERSE REACTIONS

Most common adverse reactions associated with TREMFYA are:

- Plaque Psoriasis and Psoriatic Arthritis (≥1%): upper respiratory infections, headache, injection site reactions, arthralgia, bronchitis, diarrhea, gastroenteritis, tinea infections, and herpes simplex infections. (6.1)
- Ulcerative Colitis (≥3%): injection site reactions, arthralgia, upper respiratory tract infections, headache, gastroenteritis, fatigue, pyrexia, and rash. (6.1)
- Crohn's Disease (≥3%): respiratory tract infections, abdominal pain, injection site reactions, headache, fatigue, arthralgia, diarrhea, and gastroenteritis. (6.1)

To report SUSPECTED ADVERSE REACTIONS, contact Janssen Biotech, Inc. at 1-800-526-7736 or FDA at 1-800-FDA-1088 or www.fda.gov/medwatch.

FULL PRESCRIBING INFORMATION

1 INDICATIONS AND USAGE

1.1 Plaque Psoriasis

TREMFYA is indicated for the treatment of adults and pediatric patients 6 years of age and older who also weigh at least 40 kg with moderate-to-severe plaque psoriasis and who are candidates for systemic therapy or phototherapy.

1.2 Psoriatic Arthritis

TREMFYA is indicated for the treatment of adults and pediatric patients 6 years of age and older who also weigh at least 40 kg with active psoriatic arthritis.

1.3 Ulcerative Colitis

TREMFYA is indicated for the treatment of adult patients with moderately to severely active ulcerative colitis.

1.4 Crohn's Disease

TREMFYA is indicated for the treatment of adult patients with moderately to severely active Crohn's disease.

2 DOSAGE AND ADMINISTRATION

2.1 Recommended Evaluations and Immunizations Prior to Treatment Initiation

- Evaluate patients for tuberculosis (TB) infection prior to initiating treatment with TREMFYA [see Warnings and Precautions (5.3)].
- For the treatment of ulcerative colitis or Crohn’s disease, obtain liver enzymes and bilirubin levels prior to initiating treatment with TREMFYA [see Warnings and Precautions (5.4)].
- For the treatment of plaque psoriasis or psoriatic arthritis, if clinically indicated, evaluate liver enzymes and bilirubin prior to initiating treatment with TREMFYA [see Warnings and Precautions (5.4)].
- Complete all age-appropriate vaccinations according to current immunization guidelines [see Warnings and Precautions (5.5)].

2.2 Recommended Dosage for Moderate-to-Severe Plaque Psoriasis

Administer TREMFYA by subcutaneous injection at Week 0, Week 4, and every 8 weeks thereafter.

Adults

The recommended dose is 100 mg.

Pediatric Patients 6 Years of Age and Older Who Also Weigh at Least 40 kg

The recommended dose is 100 mg.

2.3 Recommended Dosage for Active Psoriatic Arthritis

Administer TREMFYA by subcutaneous injection at Week 0, Week 4, and every 8 weeks thereafter.

TREMFYA may be administered alone or in combination with a conventional disease-modifying antirheumatic drug (e.g., methotrexate).

Adults

The recommended dose is 100 mg.

Pediatric Patients 6 Years of Age and Older Who Also Weigh at Least 40 kg

The recommended dose is 100 mg.

2.4 Recommended Dosage for Moderately to Severely Active Ulcerative Colitis and Crohn's Disease

Adults

Induction:

The recommended induction dosage of TREMFYA is:

- 200 mg administered by intravenous infusion over at least one hour at Week 0, Week 4, and Week 8 [see Dosage and Administration (2.6)] or
- 400 mg administered by subcutaneous injection (given as two consecutive injections of 200 mg each) at Week 0, Week 4, and Week 8.

Maintenance:

The recommended maintenance dosage of TREMFYA is:

- 100 mg administered by subcutaneous injection at Week 16, and every 8 weeks thereafter, or
- 200 mg administered by subcutaneous injection at Week 12, and every 4 weeks thereafter.

Use the lowest effective recommended dosage to maintain therapeutic response.

2.5 Preparation and Administration Instructions for Subcutaneous Injection

TREMFYA is available for subcutaneous use in the following presentations: prefilled pen (TREMFYA PEN), One-Press injector, and prefilled syringes [see Dosage Forms and Strengths (3) and How Supplied/Storage and Handling (16)].

- Each prefilled pen, One-Press injector, or prefilled syringe is for one time use in one patient only. Instruct patients to inject the full amount: 100 mg or 200 mg of TREMFYA (1 mL or 2 mL, respectively).
- TREMFYA is intended for use under the guidance and supervision of a healthcare professional. After proper training in subcutaneous injection technique:
  Adults
  - Adults may self-inject with the TREMFYA prefilled syringe, One-Press injector, and prefilled pen.
  - Inject into the front of the thighs, the lower abdomen except for the 2 inches around the navel, or the back of the upper arms (healthcare professional or caregiver only).
  Pediatric Patients 6 Years of Age and Older Who Also Weigh at Least 40 kg
  - Pediatric self-administration is not recommended. Administration of TREMFYA to pediatric patients with the prefilled syringe, One-Press injector and prefilled pen should be performed by a healthcare provider or by a caregiver who has received training and demonstrated proper subcutaneous injection technique.
  - Inject into the front of the thighs or the lower abdomen except for the 2 inches around the navel. For the prefilled syringe only, injection can also be given in the back of the upper arms.
- Before injection, remove TREMFYA from the refrigerator and allow to reach room temperature up to 25 °C (77 °F) (30 minutes) without removing the needle cap.
- Do not inject TREMFYA into areas where the skin is tender, bruised, red, hard, thick, scaly, or affected by psoriasis [see Instructions for Use].
- The TREMFYA Instructions for Use contains more detailed patient instructions on the preparation and administration of TREMFYA [see Instructions for Use].
- If a dose is missed, administer the dose as soon as possible. Thereafter, resume dosing at the regular scheduled time.
- Inspect TREMFYA visually for particulate matter and discoloration prior to administration. TREMFYA is a clear and colorless to light yellow solution that may contain small translucent particles. Do not use if the liquid contains large particles, is discolored or cloudy. TREMFYA does not contain preservatives; therefore, discard any unused product remaining in the prefilled pen, One-Press injector, or prefilled syringe.

2.6 Preparation and Administration Instructions for Intravenous Infusion (Moderately to Severely Active Ulcerative Colitis and Crohn's Disease)

Preparation Instructions:

1. Withdraw and then discard 20 mL of the 0.9% Sodium Chloride Injection from the 250 mL infusion bag which is equal to the volume of TREMFYA to be added.
2. Withdraw 20 mL of TREMFYA from the vial and add it to the 250 mL intravenous infusion bag of 0.9% Sodium Chloride Injection for a final concentration of 0.8 mg/mL. Gently mix the diluted solution. Discard the vial with any remaining solution.
3. Visually inspect the diluted solution for particulate matter and discoloration before infusion. Infuse the diluted solution over a period of at least one hour.
4. Use only an infusion set with an in-line, sterile, non-pyrogenic, low protein binding filter (pore size 0.2 micrometer).
5. Do not infuse TREMFYA concomitantly in the same intravenous line with other medicinal products.
6. Dispose any unused medicinal product in accordance with local requirements.

Administration Instructions:

- TREMFYA solution for intravenous infusion must be diluted, prepared, and infused by a healthcare professional using aseptic technique. TREMFYA does not contain preservatives. Each vial is for one time use in one patient only.
- Inspect TREMFYA visually for particulate matter and discoloration prior to administration. TREMFYA is a clear and colorless to light yellow solution that may contain small translucent particles. Do not use if the liquid contains large particles, is discolored, or is cloudy.

Storage of Diluted Solution:

- The diluted infusion solution may be kept at room temperature up to 25 °C (77 °F) for up to 10 hours. Storage time at room temperature begins once the diluted solution has been prepared. The infusion should be completed within 10 hours after the dilution in the infusion bag.
- Do not freeze.
- Discard any unused portion of the infusion solution.

3 DOSAGE FORMS AND STRENGTHS

TREMFYA is a clear and colorless to light yellow solution.

Subcutaneous Injection

- Injection: 100 mg/mL in a single-dose One-Press patient-controlled injector.
- Injection: 100 mg/mL in a single-dose prefilled pen (TREMFYA PEN).
- Injection: 200 mg/2 mL in a single-dose prefilled pen (TREMFYA PEN).
- Injection: 100 mg/mL in a single-dose prefilled syringe.
- Injection: 200 mg/2 mL (100 mg/mL) in a single-dose prefilled syringe.

Intravenous Infusion

- Injection: 200 mg/20 mL (10 mg/mL) solution in a single-dose vial.

4 CONTRAINDICATIONS

TREMFYA is contraindicated in patients with a history of serious hypersensitivity reaction to guselkumab or to any of the excipients [see Warnings and Precautions (5.1)].

5 WARNINGS AND PRECAUTIONS

5.1 Hypersensitivity Reactions

Serious hypersensitivity reactions, including anaphylaxis, have been reported with post market use of TREMFYA. Some cases required hospitalization. If a serious hypersensitivity reaction occurs, discontinue TREMFYA and initiate appropriate therapy.

5.2 Infections

TREMFYA may increase the risk of infection [see Adverse Reactions (6.1)].

In placebo-controlled clinical trials of up to 48 weeks in subjects with ulcerative colitis and Crohn’s disease, serious infections occurred in ≤ 2% of subjects who received TREMFYA. In the 16-week placebo-controlled trials in subjects with plaque psoriasis, the rate of serious infections for the TREMFYA group and the placebo group was ≤ 0.2%. A similar rate of serious infections was seen in placebo-controlled trials in subjects with psoriatic arthritis. The overall rates of infections were similar between subjects in the TREMFYA groups and subjects in the placebo groups in clinical trials for all indicated populations [see Adverse Reactions (6.1)].

Treatment with TREMFYA should not be initiated in patients with any clinically important active infection until the infection resolves or is adequately treated.

In patients with a chronic infection or a history of recurrent infection, consider the risks and benefits prior to prescribing TREMFYA. Instruct patients to seek medical help if signs or symptoms of clinically important chronic or acute infection occur. If a patient develops a clinically important or serious infection or is not responding to standard therapy, monitor the patient closely and discontinue TREMFYA until the infection resolves.

5.3 Tuberculosis

Evaluate patients for tuberculosis (TB) infection prior to initiating TREMFYA treatment. Do not administer TREMFYA to patients with active TB infection. Initiate treatment of latent TB prior to administering TREMFYA. Consider anti-TB therapy prior to initiating TREMFYA in patients with a past history of latent or active TB in whom an adequate course of treatment cannot be confirmed. Monitor all patients for signs and symptoms of active TB during and after TREMFYA treatment.

In clinical trials, 105 subjects with plaque psoriasis, 71 subjects with psoriatic arthritis, 43 subjects with ulcerative colitis, and 36 subjects with Crohn's disease with latent TB who were concurrently treated with TREMFYA, and appropriate TB prophylaxis did not develop active TB. In clinical trials of TREMFYA in subjects with Crohn's disease, active TB was reported in 2 subjects during treatment with TREMFYA [see Adverse Reactions (6.1)].

5.4 Hepatotoxicity

A serious adverse reaction of drug-induced liver injury was reported in a clinical trial subject with Crohn's disease following three doses of a higher than the recommended induction regimen. This subject had peak alanine aminotransferase (ALT) of 18x the upper limit of normal (ULN), aspartate aminotransferase (AST) of 11x ULN, and total bilirubin of 2.4x ULN. TREMFYA was subsequently discontinued, and the liver test abnormalities resolved following administration of corticosteroids [see Adverse Reactions (6.1)].

In patients with ulcerative colitis or Crohn's disease, evaluate liver enzymes and bilirubin at baseline, for at least 16 weeks of treatment, and periodically thereafter according to routine patient management.

In patients with plaque psoriasis or psoriatic arthritis, if clinically indicated, evaluate liver enzymes and bilirubin at baseline, and periodically thereafter according to routine patient management.

Consider other treatment options in patients with evidence of acute liver disease or cirrhosis. Prompt investigation of the cause of liver enzyme elevation is recommended to identify potential cases of drug-induced liver injury. Interrupt treatment if drug-induced liver injury is suspected, until this diagnosis is excluded. Instruct patients to seek immediate medical attention if they experience symptoms suggestive of hepatic dysfunction.

5.5 Immunizations

Avoid use of live vaccines in patients treated with TREMFYA. Medications that interact with the immune system may increase the risk of infection following administration of live vaccines. Prior to initiating therapy with TREMFYA, complete all age-appropriate vaccinations according to current immunization guidelines. No data are available on the response to live or inactive vaccines.

6 ADVERSE REACTIONS

The following adverse reactions are discussed in greater detail in other sections of labeling:

- Hypersensitivity Reactions [see Contraindications (4) and Warnings and Precautions (5.1)]
- Infections [see Warnings and Precautions (5.2)]
- Tuberculosis [see Warnings and Precautions (5.3)]
- Hepatotoxicity [see Warnings and Precautions (5.4)]

6.1 Clinical Trials Experience

Because clinical trials are conducted under widely varying conditions, adverse reaction rates observed in the clinical trials of a drug cannot be directly compared to rates in the clinical trials of another drug and may not reflect the rates observed in practice.

Adverse Reactions in Adults with Plaque Psoriasis

In clinical trials, a total of 1823 adult subjects with moderate-to-severe plaque psoriasis received TREMFYA. Of these, 1393 subjects were exposed to TREMFYA for at least 6 months and 728 subjects were exposed for at least 1 year.

Data from two placebo- and active-controlled trials (PsO1 and PsO2) in 1441 subjects (mean age 44 years; 70% males; 82% white) were pooled to evaluate the safety of TREMFYA (100 mg administered subcutaneously at Weeks 0 and 4, followed by every 8 weeks).

Weeks 0 to 16:

In the 16-week placebo-controlled period of the pooled clinical trials (PsO1 and PsO2), adverse events occurred in 49% of subjects in the TREMFYA group compared to 47% of subjects in the placebo group and 49% of subjects in the U.S. licensed adalimumab group. Serious adverse events occurred in 1.9% of subjects in the TREMFYA group (6.3 events per 100 patient-years of follow-up) compared to 1.4% of subjects in the placebo group (4.7 events per 100 patient-years of follow-up), and in 2.6% of subjects in U.S. licensed adalimumab group (9.9 events per 100 patient-years of follow-up).

Table 1 summarizes the adverse reactions that occurred at a rate of at least 1% and at a higher rate in the TREMFYA group than in the placebo group during the 16-week placebo-controlled period.

Table 1: Adverse Reactions Occurring in ≥1% of Adult Subjects with Moderate-to-Severe Plaque Psoriasis through Week 16 in Trials PsO1 and PsO2
 | TREMFYA [Subjects receiving 100 mg of TREMFYA at Week 0, Week 4, and every 8 weeks thereafter] 100 mg N=823 n (%) | Adalimumab [U.S. licensed adalimumab] N=196 n (%) | Placebo N=422 n (%)
Upper respiratory infections [Upper respiratory infections include nasopharyngitis, upper respiratory tract infection (URTI), pharyngitis, and viral URTI.] | 118 (14.3) | 21 (10.7) | 54 (12.8)
Headache [Headache includes headache and tension headache.] | 38 (4.6) | 2 (1.0) | 14 (3.3)
Injection site reactions [Injection site reactions include injection site erythema, bruising, hematoma, hemorrhage, swelling, edema, pruritus, pain, discoloration, induration, inflammation, and urticaria.] | 37 (4.5) | 15 (7.7) | 12 (2.8)
Arthralgia | 22 (2.7) | 4 (2.0) | 9 (2.1)
Diarrhea | 13 (1.6) | 3 (1.5) | 4 (0.9)
Gastroenteritis [Gastroenteritis includes gastroenteritis and viral gastroenteritis.] | 11 (1.3) | 4 (2.0) | 4 (0.9)
Tinea infections [Tinea infections include tinea pedis, tinea cruris, tinea infection, and tinea manuum infections.] | 9 (1.1) | 0 | 0
Herpes simplex infections [Herpes simplex infections include oral herpes, herpes simplex, genital herpes, genital herpes simplex, and nasal herpes simplex.] | 9 (1.1) | 0 | 2 (0.5)

Adverse reactions that occurred in < 1% but > 0.1% of subjects in the TREMFYA group and at a higher rate than in the placebo group through Week 16 in trials PsO1 and PsO2 were migraine, candida infections, and urticaria.

Specific Adverse Reactions

- Infections
  Infections occurred in 23% of subjects in the TREMFYA group compared to 21% of subjects in the placebo group through 16 weeks of treatment.
  The most common (≥ 1%) infections that occurred more frequently in the TREMFYA group than in the placebo group were upper respiratory infections, gastroenteritis, tinea infections, and herpes simplex infections; all cases were mild to moderate in severity and did not lead to discontinuation of TREMFYA. The rate of serious infections for the TREMFYA group and the placebo group was ≤ 0.2%.

- Elevated Liver Enzymes
  Elevated liver enzymes were reported more frequently in the TREMFYA group (2.6%) than in the placebo group (1.9%). Of the 21 subjects who were reported to have elevated liver enzymes in the TREMFYA group, all events except one were mild to moderate in severity and none of the events led to discontinuation of TREMFYA.

- Safety through Week 48
  Through Week 48, no new adverse reactions were identified with TREMFYA use and the frequency of the adverse reactions was similar to the safety profile observed during the first 16 weeks of treatment.

Adverse Reactions in Pediatric Subjects with Plaque Psoriasis

The safety of TREMFYA was studied in one placebo- and active-controlled clinical trial (PsO5) that included 120 pediatric subjects 6 years of age and older with moderate-to-severe plaque psoriasis [see Clinical Studies (14.1)]. The safety profile observed in pediatric subjects 6 years of age and older treated with TREMFYA up to 52 weeks was consistent with the safety profile observed in adult subjects with moderate-to-severe plaque psoriasis.

Adverse Reactions in Adults with Psoriatic Arthritis

TREMFYA was studied in two placebo-controlled trials in adult subjects with psoriatic arthritis (748 subjects on TREMFYA and 372 subjects on placebo). Of the 748 subjects who received TREMFYA, 375 subjects received TREMFYA 100 mg at Week 0, Week 4, and every 8 weeks thereafter and 373 subjects received TREMFYA 100 mg every 4 weeks. The overall safety profile observed in adult subjects with psoriatic arthritis treated with TREMFYA is generally consistent with the safety profile in adult subjects with plaque psoriasis with the addition of bronchitis and neutrophil count decreased. In the 24-week placebo-controlled period, combined across the two studies, bronchitis occurred in 1.6% of subjects in the TREMFYA q8w group and 2.9% of subjects in the TREMFYA q4w group compared to 1.1% of subjects in the placebo group. Neutrophil count decreased occurred in 0.3% of subjects in the TREMFYA q8w and 1.6% of subjects in the TREMFYA q4w group compared to 0% of subjects in the placebo group. The majority of events of neutrophil count decreased were mild, transient, not associated with infection and did not lead to discontinuation. A similar risk of infection and serious infections was seen in placebo-controlled trials in subjects with psoriatic arthritis as in subjects with plaque psoriasis.

Adverse Reactions in Adults with Ulcerative Colitis

TREMFYA was studied up to 12 weeks in adult subjects with moderately to severely active ulcerative colitis in a randomized, double-blind, placebo-controlled induction trial (UC1) and a randomized, double-blind, placebo-controlled, induction dose-finding trial (UC3; NCT04033445). Long-term safety up to 44 weeks was evaluated in subjects who responded to induction therapy in trials UC1 or UC3 in a randomized, double-blind, placebo-controlled maintenance trial (UC2). In a randomized, double-blind, placebo-controlled trial (UC4), subjects received subcutaneous TREMFYA at Weeks 0, 4, and 8 followed by one of two recommended subcutaneous TREMFYA dosing regimens for a total duration of up to 24 weeks [see Clinical Studies (14.3)].

Trials UC1, UC2 and UC3

In the induction trials (UC1 and UC3), 522 subjects received at least one dose of the TREMFYA intravenous induction regimen (i.e., 200 mg at Week 0, Week 4, and Week 8). Clinical response was defined as a decrease in modified Mayo score (mMS) of ≥30% and ≥2 points from baseline with either a ≥1 decrease from baseline in rectal bleeding subscore (RBS) or RBS of 0 or 1. In the maintenance trial (UC2), subjects who achieved clinical response after 12 weeks of TREMFYA intravenous induction treatment were randomized and received either TREMFYA 100 mg every 8 weeks (with the first dose given at Week 4 of trial UC2) or TREMFYA 200 mg every 4 weeks (with the first dose given at Week 0 of trial UC2), by subcutaneous (SC) injection for up to an additional 44 weeks.

Respiratory tract infections occurred in ≥2% of subjects treated with TREMFYA and at a higher rate than placebo (8.8% TREMFYA-treated subjects vs. 7.3% placebo-treated subjects) through Week 12 in the induction trials (UC1 and UC3). Respiratory tract infections included COVID-19, influenza, nasopharyngitis, respiratory tract infection, upper respiratory tract infection, and viral respiratory tract infection.

Adverse reactions that occurred in ≥3% of subjects treated with TREMFYA and at a higher rate than placebo through Week 44 in the maintenance trial (UC2) are shown in Table 2.

Table 2: Adverse Reactions Occurring in ≥3% of Adult Subjects with Moderately to Severely Active Ulcerative Colitis through Week 44 in Trial UC2
 | TREMFYA [Subjects receiving TREMFYA 100 mg at Week 16 and every 8 weeks thereafter or TREMFYA 200 mg at Week 12 and every 4 weeks thereafter.] 100 mg Subcutaneous Injection N=186 n (%) | TREMFYA 200 mg Subcutaneous Injection N=190 n (%) | Placebo N=192 n (%)
Injection site reactions [Injection site reactions include administration site pain, injection site hematoma, injection site hemorrhage, injection site hypersensitivity, injection site erythema, injection site pain, injection site pruritus, injection site rash, injection site reaction, and injection site urticaria.] | 2 (1.1) | 17 (8.9) [TREMFYA 200 mg was administered as two 100 mg injections.] | 2 (1)
Arthralgia | 8 (4.3) | 15 (7.9) | 13 (6.8)
Upper respiratory tract infection | 6 (3.2) | 13 (6.8) | 8 (4.2)

Trial UC4

In trial UC4, 418 subjects were enrolled, of whom 279 subjects were randomized to receive TREMFYA. Randomization was 1:1:1 to subcutaneous TREMFYA 400 mg at Weeks 0, 4, and 8 followed by subcutaneous TREMFYA 100 mg every 8 weeks (with the first dose given at Week 16) for up to an additional 8 weeks (from Week 16 through Week 24); subcutaneous TREMFYA 400 mg at Weeks 0, 4, and 8 followed by subcutaneous TREMFYA 200 mg every 4 weeks (with the first dose given at Week 12 for up to an additional 12 weeks (from Week 12 through Week 24); or placebo.

Adverse reactions reported in trial UC4 through Week 24 in ≥3% of subjects treated with either subcutaneous TREMFYA dosing regimen and at a higher rate than placebo are shown in Table 3.

Table 3: Adverse Reactions Occurring in ≥3% of Adult Subjects with Moderately to Severely Active Ulcerative Colitis through Week 24 in Trial UC4
 | TREMFYA 400 mg/100 mg Subcutaneous Injection [TREMFYA 400 mg as a subcutaneous injection at Weeks 0, 4, and 8, followed by TREMFYA 100 mg as a subcutaneous injection at Week 16 and every 8 weeks thereafter.] N=139 n (%) | TREMFYA 400 mg/200 mg Subcutaneous Injection [TREMFYA 400 mg as a subcutaneous injection at Weeks 0, 4, and 8, followed by TREMFYA 200 mg as a subcutaneous injection at Week 12 and every 4 weeks thereafter.] N=140 n (%) | Placebo N=139 n (%)
Arthralgia | 11 (7.9) | 7 (5.0) | 3 (2.2)
Upper respiratory tract infections [Upper respiratory tract infections include upper respiratory tract infection and viral upper respiratory tract infection.] | 11 (7.9) | 5 (3.6) | 9 (6.5)
Injection site reactions [Injection site reactions include injection site erythema, injection site swelling, injection site pain, injection site paresthesia, injection site edema, injection site bruising, injection site induration, injection site pruritus, application site edema, application site erythema, and application site pain.] | 7 (5.0) | 9 (6.4) | 4 (2.9)
Headache [Headache includes headache, migraine, and sinus headache.] | 8 (5.8) | 7 (5.0) | 3 (2.2)
Gastroenteritis | 4 (2.9) | 3 (2.1) | 0
Fatigue | 2 (1.4) | 4 (2.9) | 1 (0.7)
Pyrexia | 1 (0.7) | 4 (2.9) | 2 (1.4)
Rash [Rash includes rash and rash pruritic.] | 4 (2.9) | 1 (0.7) | 1 (0.7)

Specific Adverse Reactions

Infections

In the 44-week trial (UC2), serious infections occurred in 0.8% of subjects treated with TREMFYA versus 0% of subjects in the placebo group. In the 24-week trial (UC4), serious infections occurred in 1.8% of subjects treated with TREMFYA versus 0.7% of subjects in the placebo group.

Adverse Reactions in Adults with Crohn's Disease

TREMFYA was studied in four clinical trials in adult subjects with moderately to severely active Crohn's disease [see Clinical Studies (14.4)]. In two randomized, double-blind, placebo-controlled trials (CD1, CD2) and one randomized, double-blind, dose-ranging trial (CD4, NCT03466411); subjects received intravenous TREMFYA at Weeks 0, 4, and 8 followed by one of two recommended subcutaneous TREMFYA dosing regimens for a total duration of up to 48 weeks. In a randomized, double-blind, placebo-controlled trial (CD3); subjects received subcutaneous TREMFYA at Weeks 0, 4, and 8 followed by one of two recommended subcutaneous TREMFYA dosing regimens for a total duration of up to 48 weeks.

Trials CD1, CD2, and CD4

In trials CD1, CD2, and CD4; 1349 subjects were enrolled, of whom 649 were randomized to intravenous TREMFYA 200 mg at Weeks 0, 4, and 8 followed by either subcutaneous TREMFYA 100 mg every 8 weeks (with the first dose given at Week 16) for up to an additional 32 weeks (from Week 16 through Week 48) or subcutaneous TREMFYA 200 mg every 4 weeks (with the first dose given at Week 12) for up to an additional 36 weeks (from Week 12 through Week 48); and 211 subjects were randomized to receive placebo.

Through Week 12 in trials CD1, CD2, and CD4; headache (including headache, migraine, and sinus headache) was reported in ≥3% of subjects treated with intravenous TREMFYA and at a greater rate than placebo (3.4% TREMFYA-treated subjects vs. 1.9% placebo-treated subjects). In TREMFYA-treated subjects in trial CD2, one case of active extrapulmonary TB was reported between Weeks 12–48 and one case of active pulmonary TB was reported after Week 48. Both subjects had negative baseline screenings and resided in TB-endemic regions [see Warnings and Precautions (5.3)]. In general, the safety profile in subjects treated with subcutaneous TREMFYA from Week 12 up to Week 48 in these trials was generally similar to that reported with intravenous TREMFYA through Week 12.

Trial CD3

In trial CD3, 347 subjects were enrolled, of whom 230 subjects were randomized to receive TREMFYA. Randomization was 1:1:1 to subcutaneous TREMFYA 400 mg at Weeks 0, 4, and 8 followed by subcutaneous TREMFYA 100 mg every 8 weeks (with the first dose given at Week 16) for up to an additional 32 weeks (from Week 16 through Week 48); subcutaneous TREMFYA 400 mg at Weeks 0, 4, and 8 followed by subcutaneous TREMFYA 200 mg every 4 weeks (with the first dose given at Week 12) for up to an additional 36 weeks (from Week 12 through Week 48); or placebo.

Adverse reactions reported in trial CD3 through Week 48 in ≥3% of subjects treated with either subcutaneous TREMFYA dosing regimen and at a higher rate than placebo are shown in Table 4.

Table 4: Adverse Reactions Occurring in ≥3% of Adult Subjects with Moderately to Severely Active Crohn's Disease Treated with Either Recommended Subcutaneous TREMFYA Regimen through Week 48 in Trial CD3
 | TREMFYA 400 mg/100 mg Subcutaneous Injection [TREMFYA 400 mg as a subcutaneous injection at Weeks 0, 4, and 8, followed by TREMFYA 100 mg as a subcutaneous injection at Week 16 and every 8 weeks thereafter.] | TREMFYA 400 mg/200 mg Subcutaneous Injection [TREMFYA 400 mg as a subcutaneous injection at Weeks 0, 4, and 8, followed by TREMFYA 200 mg as a subcutaneous injection at Week 12 and every 4 weeks thereafter.] | Placebo
 | N=115 n (%) | N=115 n (%) | N=117 n (%)
Respiratory tract infections [Respiratory tract infections include bronchitis, COVID-19, H1N1 influenza, influenza, influenza like illness, nasopharyngitis, pneumonia, respiratory tract infection, tonsillitis, upper respiratory tract infection, and viral upper respiratory tract infection.] | 44 (38.3) | 35 (30.4) | 30 (25.6)
Abdominal pain [Abdominal pain includes abdominal pain, abdominal pain lower, and abdominal pain upper.] | 14 (12.2) | 16 (13.9) | 8 (6.8)
Injection site reactions [Injection site reactions includes application site hypersensitivity, application site pruritus, injection site edema, injection site erythema, injection site hemorrhage, injection site mass, injection site rash, injection site reaction, and injection site swelling.] | 5 (4.3) | 4 (3.5) | 0
Fatigue | 3 (2.6) | 4 (3.5) | 0
Headache [Headache includes headache and tension headache.] | 7 (6.1) | 9 (7.8) | 5 (4.3)
Arthralgia | 6 (5.2) | 5 (4.3) | 4 (3.4)
Diarrhea | 6 (5.2) | 4 (3.5) | 3 (2.6)
Gastroenteritis | 4 (3.5) | 2 (1.7) | 1 (0.9)

Specific Adverse Reactions

Infections

In the 48-week clinical trial in subjects with Crohn’s disease (CD3), serious infections occurred in 1.5% of subjects treated with TREMFYA versus 0% of subjects in the placebo group.

Elevated Liver Enzymes

Through Week 12 in CD1, CD2, and CD4; ALT ≥5× ULN was reported in 2/645 (0.3%) subjects treated with intravenous TREMFYA 200 mg at Weeks 0, 4, and 8 and 0/211 subjects treated with placebo. These elevations occurred without concomitant elevations in total bilirubin.

Through Week 48 in CD3, ALT ≥5× ULN was reported in 0/115 subjects treated with subcutaneous TREMFYA 400 mg at Weeks 0, 4, and 8 followed by subcutaneous TREMFYA 100 mg every 8 weeks; 2/115 (1.7%) subjects treated with subcutaneous TREMFYA 400 mg at Weeks 0, 4, and 8 followed by subcutaneous TREMFYA 200 mg every 4 weeks; and 0/117 subjects treated with placebo. These elevations occurred without concomitant elevations in total bilirubin.

6.2 Postmarketing Experience

The following adverse reactions have been reported during post-approval of TREMFYA. Because these reactions are reported voluntarily from a population of uncertain size, it is not always possible to reliably estimate their frequency or establish a causal relationship to TREMFYA exposure.

Immune system disorders: Hypersensitivity, including anaphylaxis [see Warnings and Precautions (5.1)]

Skin and subcutaneous tissue disorders: Rash [see Warnings and Precautions (5.1)]

7 DRUG INTERACTIONS

7.1 CYP450 Substrates

The formation of CYP450 enzymes can be altered by increased levels of certain cytokines (e.g., IL-1, IL-6, IL-10, TNFα, interferon) during chronic inflammation.

Results from an exploratory drug-drug interaction trial in subjects with moderate-to-severe plaque psoriasis suggested a low potential for clinically relevant drug interactions for drugs metabolized by CYP3A4, CYP2C9, CYP2C19 and CYP1A2 but the interaction potential cannot be ruled out for drugs metabolized by CYP2D6. However, the results were highly variable because of the limited number of subjects in the trial.

Upon initiation of TREMFYA in patients who are receiving concomitant CYP450 substrates, particularly those with a narrow therapeutic index, consider monitoring for therapeutic effect or drug concentration and consider dosage adjustment as needed [see Clinical Pharmacology (12.3)].

8 USE IN SPECIFIC POPULATIONS

8.1 Pregnancy

Pregnancy Exposure Registry

There is a pregnancy registry that monitors pregnancy outcomes in women exposed to TREMFYA during pregnancy. Patients should be encouraged to enroll in the registry by visiting www.mothertobaby.org/ongoing-study/tremfya-guselkumab, by calling 1-877-311-8972, or emailing MotherToBaby@health.ucsd.edu.

Risk Summary

Available data from literature, post-marketing reports, and ongoing pregnancy registry with TREMFYA use in pregnant women are insufficient to establish a drug-associated risk of major birth defects, miscarriage or other adverse maternal or fetal outcomes. Monoclonal antibodies are actively transported across the placenta (see Clinical Considerations).

In a combined embryofetal development and pre- and post-natal development study, no adverse developmental effects were observed in infants born to pregnant monkeys after subcutaneous administration of guselkumab during organogenesis through parturition at doses up to 18 times the exposure (AUC) in humans administered 200 mg intravenously and 16 times the exposure (AUC) to the 400 mg dose given subcutaneously. Neonatal deaths in monkeys were observed at 4 to 18 times the exposure (AUC) in humans administered 200 mg intravenously and 4 to 16 times the exposure (AUC) to the 400 mg dose given subcutaneously (see Data). The clinical significance of these nonclinical findings is unknown.

All pregnancies have a background risk of birth defect, loss, or other adverse outcomes. The background risk of major birth defects and miscarriage for the indicated population is unknown. In the U.S. general population, the estimated background risk of major birth defects and miscarriage in clinically recognized pregnancies is 2% to 4% and 15% to 20%, respectively.

Clinical Considerations

Disease-associated Maternal and Embryo/Fetal Risk

Published data suggest that the risk of adverse pregnancy outcomes in women with inflammatory bowel disease (IBD) is associated with increased disease activity. Adverse pregnancy outcomes include preterm delivery (before 37 weeks gestation), low birth weight (less than 2500 g) infants, and small for gestational age at birth.

Fetal/Neonatal Adverse Reactions

Transport of endogenous IgG antibodies across the placenta increases as pregnancy progresses and peaks during the third trimester. Therefore, TREMFYA may be present in infants exposed in utero. The potential clinical impact of guselkumab exposure in infants exposed in utero should be considered.

Data

Animal Data

In a combined embryofetal development and pre- and post-natal development study, pregnant cynomolgus monkeys were administered weekly subcutaneous doses of guselkumab from the beginning of organogenesis to parturition at a dose (50 mg/kg) resulting in exposures (AUC) 18 times the exposure in humans administered 200 mg intravenously and 16 times the human exposure at 400 mg given subcutaneously. Neonatal deaths occurred in the offspring of one control monkey, three monkeys administered guselkumab at 10 mg/kg/week (4 times the exposure (AUC) in humans administered 200 mg intravenously or 400 mg given subcutaneously) and three monkeys administered guselkumab at 50 mg/kg/week (18 times the exposure (AUC) in humans administered 200 mg intravenously and 16 times the exposure (AUC) following a 400 mg subcutaneous dose). The clinical significance of these findings is unknown. No guselkumab-related effects on functional or immunological development were observed in the infants from birth through 6 months of age.

8.2 Lactation

Risk Summary

There are no data on the presence of guselkumab in human milk, the effects on the breastfed infant, or the effects on milk production. Guselkumab was not detected in the milk of lactating cynomolgus monkeys. Endogenous maternal IgG and monoclonal antibodies are transferred into human milk. The effects of local gastrointestinal exposure and the extent of systemic exposure in the breastfed infant to guselkumab are unknown. The developmental and health benefits of breastfeeding should be considered along with the mother's clinical need for TREMFYA and any potential adverse effects on the breastfed infant from TREMFYA or from the underlying maternal condition.

8.4 Pediatric Use

Plaque Psoriasis

The safety and effectiveness of TREMFYA for the treatment of moderate-to-severe plaque psoriasis have been established in pediatric patients 6 years of age and older who are candidates for systemic therapy or phototherapy [see Adverse Reactions (6.1) and Clinical Studies (14.1)].

The safety and effectiveness of TREMFYA have not been established in pediatric patients with plaque psoriasis who are younger than 6 years of age.

Psoriatic Arthritis

The safety and effectiveness of TREMFYA have been established for treatment of active psoriatic arthritis in pediatric patients 6 years of age and older.

Use of TREMFYA in this age group is supported by evidence from adequate and well controlled trials of TREMFYA in adults with plaque psoriasis and psoriatic arthritis, pharmacokinetic data from adult subjects with plaque psoriasis and psoriatic arthritis and pediatric subjects with plaque psoriasis, and safety data from a clinical trial in 120 subjects 6 to 17 years of age with plaque psoriasis. The observed pre-dose (trough) concentrations are generally comparable between adult subjects with plaque psoriasis, adult subjects with psoriatic arthritis and pediatric subjects with plaque psoriasis, and the systemic exposure is expected to be comparable between adult and pediatric patients with psoriatic arthritis [see Adverse Reactions (6.1), Clinical Pharmacology (12.3), and Clinical Studies (14.1, 14.2)].

The safety and effectiveness of TREMFYA have not been established in pediatric patients with psoriatic arthritis who are younger than 6 years of age.

Ulcerative Colitis

The safety and effectiveness of TREMFYA have not been established in pediatric patients with ulcerative colitis.

Crohn's Disease

The safety and effectiveness of TREMFYA have not been established in pediatric patients with Crohn’s disease.

8.5 Geriatric Use

Of the 5723 subjects with plaque psoriasis, psoriatic arthritis, ulcerative colitis, or Crohn's disease exposed to TREMFYA, a total of 313 subjects were 65 years or older, and 32 subjects were 75 years or older. Clinical studies of TREMFYA, within each indication, did not include sufficient numbers of subjects 65 years of age and older to determine whether they respond differently from younger adult subjects.

No clinically meaningful differences in the pharmacokinetics of guselkumab were observed based on age [see Clinical Pharmacology (12.3)].

11 DESCRIPTION

Guselkumab, an interleukin-23 antagonist, is a human immunoglobulin G1 lambda (IgG1λ) monoclonal antibody. Guselkumab is produced in a mammalian cell line using recombinant DNA technology and has an approximate molecular weight of approximately 147 kDa.

TREMFYA® (guselkumab) injection is a sterile, preservative free, clear, and colorless to light yellow solution.

TREMFYA for Subcutaneous Injection

Available as a 100 mg/mL solution in a 1 mL or 2 mL glass prefilled syringe, in a 1 mL or 2 mL prefilled pen (TREMFYA PEN), or in a 1 mL One-Press patient-controlled injector for subcutaneous use.

- Each TREMFYA 1 mL prefilled syringe, prefilled pen (TREMFYA PEN), or One-Press patient-controlled injector delivers 100 mg guselkumab, L-histidine (0.6 mg), L-histidine monohydrochloride monohydrate (1.5 mg), polysorbate 80 (0.5 mg), sucrose (79 mg) and water for injection at pH 5.8.
- Each TREMFYA 2 mL prefilled syringe or prefilled pen (TREMFYA PEN) delivers 200 mg guselkumab, L-histidine (1.2 mg), L-histidine monohydrochloride monohydrate (3 mg), polysorbate 80 (1 mg), sucrose (158 mg) and water for injection at pH 5.8.

TREMFYA for Intravenous Infusion

Available as 10 mg/mL solution in a 20 mL single-dose vial for intravenous use.

Each TREMFYA 20 mL vial delivers 200 mg guselkumab, EDTA disodium dihydrate (0.4 mg), L-histidine (11.3 mg), L-histidine monohydrochloride monohydrate (26.6 mg), L-methionine (8 mg), polysorbate 80 (10 mg), sucrose (1700 mg) and water for injection at pH 5.8.

12 CLINICAL PHARMACOLOGY

12.1 Mechanism of Action

Guselkumab is a human monoclonal IgG1λ antibody that selectively binds to the p19 subunit of interleukin 23 (IL-23) and inhibits its interaction with the IL-23 receptor. IL-23 is a naturally occurring cytokine that is involved in normal inflammatory and immune responses. Guselkumab inhibits the release of proinflammatory cytokines and chemokines.

12.2 Pharmacodynamics

In evaluated adult subjects with moderate-to-severe plaque psoriasis, guselkumab reduced serum levels of IL-17A, IL-17F and IL-22 relative to pre-treatment levels based on exploratory analyses of the pharmacodynamic markers.

In evaluated adult subjects with active psoriatic arthritis, serum levels of acute phase proteins C-reactive protein, serum amyloid A and IL-6, and Th17 effector cytokines IL-17A, IL-17F and IL-22 were elevated at baseline. Serum levels of these proteins measured at Week 4 and Week 24 were decreased compared to baseline following guselkumab treatment at Week 0, Week 4, and every 8 weeks thereafter.

The relationship between these pharmacodynamic markers and the mechanism(s) by which guselkumab exerts its clinical effects is unknown.

12.3 Pharmacokinetics

Guselkumab exhibited linear pharmacokinetics in healthy adult subjects and adult subjects with plaque psoriasis following subcutaneous injections. In subjects with plaque psoriasis, following subcutaneous administration of 100 mg of TREMFYA at Weeks 0 and 4, and every 8 weeks thereafter, mean steady-state trough serum guselkumab concentration was approximately 1.2 mcg/mL.

The pharmacokinetics of guselkumab in adult subjects with psoriatic arthritis was similar to that in adult subjects with plaque psoriasis. Following subcutaneous administration of 100 mg of TREMFYA at Weeks 0, 4, and every 8 weeks thereafter, mean steady-state trough serum guselkumab concentration was approximately 1.2 mcg/mL.

Following subcutaneous maintenance dosing of 100 mg TREMFYA every 8 weeks or 200 mg TREMFYA every 4 weeks in adult subjects with ulcerative colitis, mean steady-state trough serum guselkumab concentrations were approximately 1.4 mcg/mL and 10.7 mcg/mL, respectively.

Following subcutaneous maintenance dosing of 100 mg TREMFYA every 8 weeks, or 200 mg TREMFYA every 4 weeks, in adult subjects with Crohn's disease mean steady-state trough serum guselkumab concentrations were approximately 1.2 mcg/mL and 10.1 mcg/mL, respectively.

Absorption

Following a single 100 mg subcutaneous injection in healthy adult subjects, guselkumab reached a mean (± SD) maximum serum concentration of 8.09 ± 3.68 mcg/mL by approximately 5.5 days post dose. The absolute bioavailability of guselkumab following a single 100 mg subcutaneous injection was estimated to be approximately 49% in healthy adult subjects.

Following the recommended intravenous induction dose regimen of TREMFYA 200 mg at Weeks 0, 4, and 8, mean (± SD) peak serum guselkumab concentration at Week 8 was 68.3 ± 17.3 mcg/mL in adult subjects with ulcerative colitis.

Following the recommended subcutaneous induction dose regimen of TREMFYA 400 mg at Weeks 0, 4, and 8, mean (± SD) peak serum guselkumab concentration was estimated to be 28.8 ± 8.8 mcg/mL in adult subjects with ulcerative colitis. The total systemic exposure (AUC) after the recommended induction dose regimen was similar following subcutaneous and intravenous induction.

Following the recommended intravenous induction dose regimen of TREMFYA 200 mg at Weeks 0, 4, and 8, mean (± SD) peak serum guselkumab concentration at Week 8 was 70.5 ± 24.5 mcg/mL in adult subjects with Crohn's disease.

Following the recommended subcutaneous induction dose regimen of TREMFYA 400 mg at Weeks 0, 4, and 8, mean (± SD) peak serum guselkumab concentration was estimated to be 27.7 ± 9.1 mcg/mL in adult subjects with Crohn's disease. The total systemic exposure (AUC) after the recommended induction dose regimen was similar following subcutaneous and intravenous induction.

Distribution

In adult subjects with plaque psoriasis, apparent volume of distribution was 13.5 L. In adult subjects with ulcerative colitis, apparent volume of distribution at steady-state was 10.1 L. In adult subjects with Crohn's disease, apparent volume of distribution at steady-state was 11.4 L.

Elimination

Apparent clearance in adult subjects with plaque psoriasis was 0.516 L/day. Mean half-life of guselkumab was approximately 15 to 18 days in subjects with plaque psoriasis across trials.

The apparent clearance in adult subjects with ulcerative colitis was 0.531 L/day. Mean half-life of guselkumab was approximately 17 days in subjects with ulcerative colitis.

The apparent clearance in adult subjects with Crohn's disease was 0.568 L/day. Mean half-life of guselkumab was approximately 17 days in subjects with Crohn's disease.

Metabolism

The exact pathway through which guselkumab is metabolized has not been characterized. As a human IgG monoclonal antibody, guselkumab is expected to be degraded into small peptides and amino acids via catabolic pathways in the same manner as endogenous IgG.

Specific Populations

Geriatric Subjects

No apparent differences in clearance were observed in subjects ≥ 65 years of age compared to subjects < 65 years of age, suggesting no dose adjustment is needed for elderly subjects. Clearance and volume of distribution of guselkumab increases as body weight increases, however, observed clinical trial data indicate that dose adjustment for body weight is not warranted. No specific trials have been conducted to determine the effect of renal or hepatic impairment on the pharmacokinetics of guselkumab.

Pediatric Subjects

In trial PsO5, steady-state serum concentrations of guselkumab were achieved by Week 20 in pediatric subjects 6 years of age and older with moderate-to-severe plaque psoriasis.

Overall, the observed guselkumab trough concentrations in pediatric subjects 6 years of age and older and also weighing at least 40 kg with plaque psoriasis were within range of those observed for adult subjects with plaque psoriasis and adult subjects with psoriatic arthritis after administration of TREMFYA.

Drug Interactions

Population pharmacokinetic analyses indicated that concomitant use of NSAIDs, oral corticosteroids and conventional DMARDs such as methotrexate (MTX), azathioprine (AZA), and 6-mercaptopurine (6-MP), did not affect the clearance of guselkumab.

Cytochrome P450 Substrates

The effects of guselkumab on the pharmacokinetics of midazolam (metabolized by CYP3A4), warfarin (metabolized by CYP2C9), omeprazole (metabolized by CYP2C19), dextromethorphan (metabolized by CYP2D6), and caffeine (metabolized by CYP1A2) were evaluated in an exploratory study with 6 to 12 evaluable subjects with moderate-to-severe plaque psoriasis. Changes in AUCinf of midazolam, S-warfarin, omeprazole, and caffeine after a single dose of guselkumab were not clinically relevant. For dextromethorphan, changes in AUCinf after guselkumab were not clinically relevant in 9 out of 10 subjects; however, a 2.9-fold change in AUCinf was observed in one individual [see Drug Interactions (7.1)].

12.6 Immunogenicity

The observed incidence of anti-drug antibodies is highly dependent on the sensitivity and specificity of the assay. Differences in assay methods preclude meaningful comparisons of the incidence of anti-drug antibodies in the studies described below with the incidence of anti-drug antibodies in other studies, including those of guselkumab or of other guselkumab products.

Plaque Psoriasis

Adult Subjects

Up to Week 52, approximately 6% of adult subjects treated with TREMFYA developed antidrug antibodies. Of the subjects who developed antidrug antibodies, approximately 7% had antibodies that were classified as neutralizing antibodies. Among the 46 subjects who developed antibodies to guselkumab and had evaluable data, 21 subjects exhibited lower trough levels of guselkumab, including one subjects who experienced loss of efficacy after developing high antibody titers. Up to Week 156, approximately 9% of subjects treated with TREMFYA developed antidrug antibodies and of these subjects approximately 6% were classified as neutralizing antibodies. However, antibodies to guselkumab were generally not associated with changes in clinical response or development of injection-site reactions.

Pediatric Subjects

Up to Week 44, 18% (n=21/114) of pediatric subjects 6 years of age and older treated with TREMFYA developed anti-drug antibodies, none of the anti-drug antibodies were classified as neutralizing. The development of antibodies to guselkumab did not impact the pharmacokinetics of guselkumab and was not associated with changes in clinical response or development of injection-site reactions. However, the small number of subjects who were positive for antibodies to guselkumab limits definitive conclusions.

Psoriatic Arthritis

Up to Week 24, 2% (n=15) of adult subjects treated with TREMFYA developed antidrug antibodies. Of these subjects, 1 had antibodies that were classified as neutralizing antibodies. Overall, the small number of subjects who were positive for antibodies to guselkumab limits definitive conclusion of the effect of immunogenicity on the pharmacokinetics, efficacy, and safety of guselkumab.

Ulcerative Colitis

Up to Week 56 in trials UC1, UC2 and UC3, 11% (48/435) of adult subjects treated with TREMFYA at the recommended dosages developed antidrug antibodies. Of these subjects who tested positive for anti-guselkumab antibodies and were evaluable for neutralizing antibodies, 16% (6/38) had antibodies that were classified as neutralizing antibodies. Two subjects with the highest antibody titers exhibited low trough levels of guselkumab. Up to Week 24 in UC4, 9% (24/279) of subjects treated with TREMFYA developed antidrug antibodies. Of the subjects who tested positive for anti-guselkumab antibodies and were evaluable for neutralizing antibodies 13% (2/16) had antibodies that were classified as neutralizing antibodies. There was no identified clinically significant effect of antidrug antibodies on injection site reactions, or effectiveness of guselkumab, over the treatment duration of 56 weeks (trials UC1, UC2 and UC3) or 24 weeks (trial UC4).

Crohn's Disease

Up to Week 48 in trials CD1, CD2, and CD4; 5% (30/634) of adult subjects treated with a recommended dosage of TREMFYA developed antidrug antibodies. Of the subjects who tested positive for anti-guselkumab antibodies and were evaluable for neutralizing antibodies, 5% (1/22) had antibodies that were classified as neutralizing antibodies. Up to Week 48 in CD3, 9% (24/273) of subjects treated with TREMFYA developed antidrug antibodies. Of the subjects who tested positive for anti-guselkumab antibodies and were evaluable for neutralizing antibodies, none had antibodies that were classified as neutralizing antibodies. There were no identified clinically significant effects of antidrug antibodies on pharmacokinetics, injection site reactions, or effectiveness of guselkumab, over the treatment duration of 48 weeks.

13 NONCLINICAL TOXICOLOGY

13.1 Carcinogenesis, Mutagenesis, Impairment of Fertility

Animal studies have not been conducted to evaluate the carcinogenic or mutagenic potential of TREMFYA.

No effects on fertility parameters were observed after male guinea pigs were subcutaneously administered guselkumab at a dose of 25 mg/kg twice weekly (6 times the exposure (AUC) in humans administered 200 mg intravenously and 5 times the exposure (AUC) at the 400 mg subcutaneous dose).

No effects on fertility parameters were observed after female guinea pigs were subcutaneously administered guselkumab at doses up to 100 mg/kg twice weekly (12 times the exposure (AUC) in humans administered 200 mg intravenously and 10 times the exposure (AUC) at the 400 mg subcutaneous dose).

14 CLINICAL STUDIES

14.1 Clinical Studies in Plaque Psoriasis

Adults with Moderate-to-Severe Plaque Psoriasis

Four multicenter, randomized, double-blind trials (PsO1 [NCT02207231], PsO2 [NCT02207244], PsO3 [NCT02203032], and PsO4 [NCT02905331]) enrolled subjects 18 years of age and older with moderate-to-severe plaque psoriasis who were eligible for systemic therapy or phototherapy. Subjects had an Investigator's Global Assessment (IGA) score of ≥3 ("moderate") on a 5-point scale of overall disease severity, a Psoriasis Area and Severity Index (PASI) score ≥12, and a minimum affected body surface area (BSA) of 10%. Subjects with guttate, erythrodermic, or pustular psoriasis were excluded.

Trials PsO1 and PsO2

In trials PsO1 and PsO2, 1443 subjects were randomized to either TREMFYA (100 mg at Weeks 0 and 4 and every 8 weeks thereafter) administered with a prefilled syringe, placebo or U.S. licensed adalimumab (80 mg at Week 0 and 40 mg at Week 1, followed by 40 mg every other week thereafter).

Both trials assessed the responses at Week 16 compared to placebo for the two co-primary endpoints:

- the proportion of subjects who achieved an IGA score of 0 ("cleared") or 1 ("minimal");
- the proportion of subjects who achieved at least a 90% reduction from baseline in the PASI composite score (PASI 90).

Comparisons between TREMFYA and U.S. licensed adalimumab were secondary endpoints at the following time points:

- at Week 16 (trials PsO1 and PsO2), the proportions of subjects who achieved an IGA score of 0 or 1, a PASI 90, and a PASI 75 response;
- at Week 24 (trials PsO1 and PsO2), and at Week 48 (trial PsO1), the proportions of subjects achieving an IGA score of 0, an IGA score of 0 or 1, and a PASI 90 response.

Other evaluated outcomes included improvement in psoriasis symptoms assessed on the Psoriasis Symptoms and Signs Diary (PSSD) and improvements in psoriasis of the scalp at Week 16.

In both trials, subjects were predominantly men and White, with a mean age of 44 years and a mean weight of 90 kg. At baseline, subjects had a median affected BSA of approximately 21%, a median PASI score of 19, and 18% had a history of psoriatic arthritis. Approximately 24% of subjects had an IGA score of 4 ("severe"). In both trials, 23% had received prior biologic systemic therapy.

Clinical Response

Table 5 presents the efficacy results at Week 16 in trials PsO1 and PsO2.

Table 5: Efficacy Results at Week 16 in Adults with Moderate-to-Severe Plaque Psoriasis in Trials PsO1 and PsO2 (NRI [NRI = Non-Responder Imputation])
 | Trial PsO1 |  | Trial PsO2
Endpoint | Placebo (N=174) n (%) | TREMFYA (N=329) n (%) | Placebo (N=248) n (%) | TREMFYA (N=496) n (%)
IGA response of 0/1 [Co-Primary Endpoints] , [IGA response of 0 ("cleared") or 1 ("minimal")] | 12 (7) | 280 (85) | 21 (8) | 417 (84)
PASI 90 response | 5 (3) | 241 (73) | 6 (2) | 347 (70)

Table 6 presents the results of an analysis of all the North America sites (i.e., U.S. and Canada), demonstrating superiority of TREMFYA to U.S. licensed adalimumab.

Table 6: Efficacy Results in Adults with Moderate-to-Severe Plaque Psoriasis in Trials PsO1 and PsO2 (NRI [NRI = Non-Responder Imputation])
 | Trial PsO1 |  | Trial PsO2
Endpoint | TREMFYA (N=115) [Subjects from sites in the United States and Canada] n (%) | Adalimumab [U.S. licensed adalimumab] (N=115) n (%) | TREMFYA (N=160) n (%) | Adalimumab (N=81) n (%)
IGA response of 0/1 ("cleared" or "minimal")
Week 16 | 97 (84) | 70 (61) | 119 (74) | 50 (62)
Week 24 | 97 (84) | 62 (54) | 119 (74) | 46 (57)
Week 48 | 91 (79) | 62 (54) | NA | NA
IGA response of 0 ("cleared")
Week 24 | 61 (53) | 27 (23) | 76 (48) | 23 (28)
Week 48 | 54 (47) | 28 (24) | NA | NA
PASI 75 response
Week 16 | 105 (91) | 80 (70) | 132 (83) | 51 (63)
PASI 90 response
Week 16 | 84 (73) | 47 (41) | 102 (64) | 34 (42)
Week 24 | 92 (80) | 51 (44) | 113 (71) | 41 (51)
Week 48 | 84 (73) | 53 (46) | NA | NA

An improvement was seen in psoriasis involving the scalp in subjects randomized to TREMFYA compared to placebo at Week 16.

Examination of age, gender, race, body weight, and previous treatment with systemic or biologic agents did not identify differences in response to TREMFYA among these subgroups.

Maintenance and Durability of Response

To evaluate maintenance and durability of response (trial PsO2), subjects randomized to TREMFYA at Week 0 and who were PASI 90 responders at Week 28 were re-randomized to either continue treatment with TREMFYA every 8 weeks or be withdrawn from therapy (i.e., receive placebo).

At Week 48, 89% of subjects who continued on TREMFYA maintained PASI 90 compared to 37% of subjects who were re-randomized to placebo and withdrawn from TREMFYA. For responders at Week 28 who were re-randomized to placebo and withdrawn from TREMFYA, the median time to loss of PASI 90 was approximately 15 weeks.

Patient Reported Outcomes

Greater improvements in symptoms of psoriasis (itch, pain, stinging, burning and skin tightness) at Week 16 in TREMFYA compared to placebo were observed in both trials based on the Psoriasis Symptoms and Signs Diary (PSSD). Greater proportions of subjects on TREMFYA compared to U.S. licensed adalimumab achieved a PSSD symptom score of 0 (symptom-free) at Week 24 in both trials.

Trial PsO3

Trial PsO3 [NCT02203032] evaluated the efficacy of 24 weeks of treatment with TREMFYA in subjects (N=268) who had not achieved an adequate response, defined as IGA ≥2 at Week 16 after initial treatment with U.S. licensed ustekinumab (dosed 45 mg or 90 mg according to the subject's baseline weight at Week 0 and Week 4). These subjects were randomized to either continue with U.S. licensed ustekinumab treatment every 12 weeks or switch to TREMFYA 100 mg at Weeks 16, 20, and every 8 weeks thereafter. Baseline characteristics for randomized subjects were similar to those observed in PsO1 and PsO2.

In subjects with an inadequate response (IGA ≥2 at Week 16 to U.S. licensed ustekinumab), greater proportions of subjects on TREMFYA compared to U.S. licensed ustekinumab achieved an IGA score of 0 or 1 with a ≥2 grade improvement at Week 28 (31% vs. 14%, respectively; 12 weeks after randomization).

Trial PsO4

Trial PsO4 [NCT02905331] evaluated the efficacy, safety, and pharmacokinetics of TREMFYA administered with the One-Press injector. In this trial, 78 subjects were randomized to receive either TREMFYA (100 mg at Weeks 0 and 4 and every 8 weeks thereafter) [N=62], or placebo [N=16]. Baseline characteristics for subjects were comparable to those observed in trials PsO1 and PsO2. The co-primary endpoints were the same as those for trials PsO1 and PsO2. Secondary endpoints included the proportion of subjects who achieved an IGA score of 0 at Week 16 and the proportion of subjects who achieved a PASI 100 response at Week 16.

A greater proportion of subjects in the guselkumab group achieved an IGA score of 0 or 1 or a PASI 90 response at Week 16 (81% and 76%, respectively) than in the placebo group (0% for both endpoints). The proportion of subjects who achieved an IGA score of 0 at Week 16 was higher in the guselkumab group compared to the placebo group (56% vs. 0%). The proportion of subjects who achieved a PASI 100 response at Week 16 was higher in the guselkumab group compared to the placebo group (50% vs. 0%).

Pediatric Subjects with Moderate-to-Severe Plaque Psoriasis

Trial PsO5

One multicenter, randomized, placebo and active biological comparator-controlled trial (PsO5 [NCT03451851]) enrolled 120 subjects 6 years to 17 years of age with moderate-to-severe plaque psoriasis who were candidates for systemic therapy or phototherapy and inadequately controlled by phototherapy and/or topical therapies.

In trial PsO5, 92 subjects were randomized to receive subcutaneous injection of either TREMFYA (N=41) or placebo (N=25) at Weeks 0, 4, and 12 or an active biological comparator (N=26). An additional 28 subjects enrolled in a TREMFYA open-label arm. Subjects with a body weight of 70 kg or more received 100 mg of TREMFYA. Subjects with a body weight less than 70 kg received doses according to their weight.

Subjects had an IGA score of ≥3 ("moderate") on a 5-point scale of overall disease severity, a PASI ≥12, and a minimum affected BSA of ≥10%, and at least one of the following: 1) very thick lesions, 2) clinically relevant facial, genital, or hand/foot involvement, 3) PASI ≥20, 4) BSA >20%, or 5) IGA=4 ("severe"). Subjects with guttate, erythrodermic, or pustular psoriasis were excluded.

Of the 92 subjects in the controlled part of the trial, 55% of subjects were male, 85% were White, 4% were Asian, and 4% were Black or African American. For ethnicity, 95% of subjects identified as Not Hispanic or Latino and 5% of subjects identified as Hispanic or Latino. Subjects had a mean body weight of 57 kg, a mean age of 13 years, and a third of the subjects were less than 12 years of age. At baseline, subjects had a median affected BSA of 20%, a median PASI score of 17, and 3% had a history of psoriatic arthritis. Approximately 22% of subjects had an IGA score of 4 ("severe"). Prior phototherapy or prior conventional systemic therapy was received by 32% of subjects and prior biologic systemic therapy was received by 10% of subjects.

The responses at Week 16 were compared to placebo for the two co-primary endpoints:

- the proportion of subjects who achieved an IGA score of 0 ("cleared") or 1 ("minimal");
- the proportion of subjects who achieved a PASI 90 response.

Other evaluated outcomes included the proportion of subjects who achieved PASI 75, IGA score of 0 ("cleared") and PASI 100 at Week 16.

Clinical Response

Table 7 presents the efficacy results at Week 16 in trial PsO5.

Table 7: Efficacy Results at Week 16 in Pediatric Subjects 6 Years of Age and Older with Moderate-to-Severe Plaque Psoriasis in Trial PsO5 (NRI [NRI = Non-Responder Imputation])
Endpoint | Trial PsO5
 | Placebo (N=25) n (%) | TREMFYA (N=41) n (%) | Treatment Difference (95% CI)
IGA response of 0/1 [Co-primary endpoint] , [IGA response of 0 ("cleared") or 1 ("minimal")] | 4 (16) | 27 (66) | 50 (26, 69)
IGA response of 0 (cleared) | 1 (4) | 16 (39) | 35 (11, 57)
PASI 75 response | 5 (20) | 31 (76) | 56 (32, 74)
PASI 90 response | 4 (16) | 23 (56) | 40 (16, 61)
PASI 100 response | 0 | 14 (34) | 34 (10, 56)

14.2 Clinical Studies in Adults with Psoriatic Arthritis

The safety and efficacy of TREMFYA were assessed in 2 randomized, double-blind, placebo-controlled trials (PsA1 [NCT03162796] and PsA2 [NCT03158285]) in 1120 adult subjects with active psoriatic arthritis (PsA) (≥3 swollen joints, ≥3 tender joints, and a C-reactive protein (CRP) level of ≥0.3 mg/dL in PsA1 and ≥5 swollen joints, ≥5 tender joints, and a CRP level of ≥0.6 mg/dL in PsA2) who had inadequate response to standard therapies (e.g., conventional DMARDs [cDMARDs]), apremilast, or nonsteroidal anti-inflammatory drugs [NSAIDs]). Subjects in these trials had a diagnosis of PsA for at least 6 months based on the Classification criteria for Psoriatic Arthritis (CASPAR) and a median duration of PsA of 4 years at baseline.

In trial PsA1, approximately 31% of subjects had been previously treated with up to 2 anti-tumor necrosis factor alpha (anti-TNFα) agents whereas in trial PsA2, all subjects were biologic naïve. Approximately 58% of subjects from both trials had concomitant methotrexate (MTX) use. Subjects with different subtypes of PsA were enrolled in both trials, including polyarticular arthritis with the absence of rheumatoid nodules (40%), spondylitis with peripheral arthritis (30%), asymmetric peripheral arthritis (23%), distal interphalangeal involvement (7%) and arthritis mutilans (1%). At baseline, over 65% and 42% of the subjects had enthesitis and dactylitis, respectively and 79% had ≥3% body surface area (BSA) psoriasis skin involvement.

Trial PsA1 evaluated 381 subjects who were treated with placebo SC, TREMFYA 100 mg SC at Weeks 0, 4 and every 8 weeks (q8w) thereafter, or TREMFYA 100 mg SC every 4 weeks (q4w). Trial PsA2 evaluated 739 subjects who were treated with placebo SC, TREMFYA 100 mg SC at Weeks 0, 4 and q8w thereafter, or TREMFYA 100 mg SC q4w. The primary endpoint in both trials was the percentage of subjects achieving an ACR20 response at Week 24.

Clinical Response

In both trials, subjects treated with TREMFYA 100 mg q8w demonstrated a greater clinical response including ACR20, compared to placebo at Week 24 (Tables 8 and 9). Similar responses were seen regardless of prior anti-TNFα exposure in PsA1, and in both trials similar responses were seen regardless of concomitant cDMARD use, previous treatment with cDMARDs, gender and body weight.

Table 8: Percent of Adult Subjects with Active Psoriatic Arthritis with ACR Responses in Trial PsA1
 | Placebo (N=126) | TREMFYA 100 mg q8w (N=127)
 | Response Rate | Response Rate | Difference from Placebo (95% CI)
ACR 20 response [Subjects with missing data at a visit were imputed as non-responders at that visit. Subjects who met escape criteria (less than 5% improvement in both tender and swollen joint counts) at Week 16 were allowed to initiate or increase the dose of the permitted concomitant medication and remained on the randomized group. Subjects who initiated or increased the dose of non-biologic DMARD or oral corticosteroids over baseline, discontinued study/study medication or initiated protocol prohibited medications/therapies for PsA prior to a visit were considered non-responders at that visit.]
Week 16 | 25% | 52% | 27 (15, 38)
Week 24 | 22% | 52% | 30 (19, 41)
ACR 50 response
Week 16 | 13% | 23% | 10 (1, 19)
Week 24 | 9% | 30% | 21 (12, 31)
ACR 70 response
Week 16 | 6% | 8% | 2 (-4, 8)
Week 24 | 6% | 12% | 6 (-0.3, 13)

Table 9: Percent of Adult Subjects with Active Psoriatic Arthritis with ACR Responses in Trial PsA2
 | Placebo (N=246) | TREMFYA 100 mg q8w (N=248)
 | Response Rate | Response Rate | Difference from Placebo (95% CI)
ACR 20 response [Subjects with missing data at a visit were imputed as non-responders at that visit. Subjects who met escape criteria (less than 5% improvement in both tender and swollen joint counts) at Week 16 were allowed to initiate or increase the dose of the permitted concomitant medication and remained on the randomized group. Subjects who initiated or increased the dose of non-biologic DMARD or oral corticosteroids over baseline, discontinued study/study medication or initiated protocol prohibited medications/therapies for PsA prior to a visit were considered non-responders at that visit.]
Week 16 | 34% | 55% | 22 (13, 30)
Week 24 | 33% | 64% | 31 (23, 40)
ACR 50 response
Week 16 | 9% | 29% | 19 (13, 26)
Week 24 | 14% | 32% | 17 (10, 24)
ACR 70 response
Week 16 | 1% | 14% | 13 (9, 17)
Week 24 | 4% | 19% | 15 (9, 20)

The percentage of subjects achieving ACR20 response in PsA2 by visit is shown in Figure 1.

Figure 1: Percentage of Adult Subjects with Active Psoriatic Arthritis Achieving ACR 20 Response by Visit Through Week 24 in Trial PsA2

The results of the components of the ACR response criteria are shown in Table 10.

Table 10: Mean change (SD [SD= standard deviation]) from Baseline in ACR Component Scores at Week 16 and 24 based on Observed Data in Trials PsA1 and PsA2
 | Trial PsA1 |  | Trial PsA2
 | Placebo (N=126) | TREMFYA 100 mg q8w (N=127) | Placebo N=246 | TREMFYA 100 mg q8w (N=248)
No. of Swollen Joints
Baseline | 10.1 (7.1) | 10.9 (9.3) | 12.3 (6.9) | 11.7 (6.8)
Mean change at Week 16 | -4.2 (7.0) | -7.3 (7.0) | -5.8 (7.1) | -7.2 (6.0)
Mean change at Week 24 | -5.1 (6.9) | -7.3 (8.0) | -6.4 (7.2) | -8.1 (6.1)
No. of Tender Joints
Baseline | 19.8 (14.4) | 20.2 (14.5) | 21.6 (13.1) | 19.8 (11.9)
Mean change at Week 16 | -4.5 (10.8) | -10.2 (10.4) | -6.8 (10.5) | -9.0 (9.4)
Mean change at Week 24 | -6.8 (13.0) | -10.5 (12.0) | -7.3 (11.2) | -10.4 (9.5)
Patient's Assessment of Pain [Assessment based on Visual Analog Scale (cm) with the left end indicating "no pain" (for patient's assessment of pain), "very well" (for patient global assessment), or "no arthritis activity" (for physician global assessment) and the right end indicating "the worst possible pain" (for patient assessment of pain), "poor" (for patient global assessment), or "extremely active arthritis (for physician global assessment).]
Baseline | 5.8 (2.2) | 6.0 (2.1) | 6.3 (1.8) | 6.3 (2.0)
Mean change at Week 16 | -0.8 (2.3) | -1.7 (2.4) | -0.9 (2.3) | -2.2 (2.5)
Mean change at Week 24 | -0.7 (2.4) | -2.2 (2.6) | -1.1 (2.4) | -2.5 (2.5)
Patient Global Assessment
Baseline | 6.1 (2.2) | 6.5 (2.0) | 6.5 (1.8) | 6.5 (1.9)
Mean change at Week 16 | -1.0 (2.3) | -2.0 (2.6) | -1.0 (2.3) | -2.3 (2.6)
Mean change at Week 24 | -0.9 (2.5) | -2.5 (2.7) | -1.2 (2.6) | -2.5 (2.5)
Physician Global Assessment
Baseline | 6.3 (1.7) | 6.2 (1.7) | 6.7 (1.5) | 6.6 (1.6)
Mean change at Week 16 | -1.9 (2.2) | -2.9 (2.4) | -2.1 (2.2) | -3.5 (2.3)
Mean change at Week 24 | -2.2 (2.3) | -3.5 (2.4) | -2.5 (2.3) | -3.8 (2.3)
Disability Index (HAQ-DI) [Disability Index of the Health Assessment Questionnaire; 0 = no difficulty to 3 = inability to perform, measures the patient's ability to perform the following: dressing, arising, eating, walking, hygiene, reaching, gripping, and activities of daily living]
Baseline | 1.2 (0.7) | 1.2 (0.6) | 1.3 (0.6) | 1.3 (0.6)
Mean change at Week 16 | -0.1 (0.5) | -0.3 (0.5) | -0.1 (0.5) | -0.3 (0.5)
Mean change at Week 24 | -0.1 (0.5) | -0.3 (0.6) | -0.2 (0.5) | -0.4 (0.5)
CRP (mg/dL)
Baseline | 1.4 (1.9) | 1.6 (2.4) | 2.1 (2.7) | 2.0 (2.4)
Mean change at Week 16 | -0.2 (1.5) | -0.6 (2.2) | -0.6 (2.5) | -1.0 (2.2)
Mean change at Week 24 | -0.0 (2.8) | -0.7 (2.1) | -0.5 (2.5) | -1.1 (2.2)

Treatment with TREMFYA resulted in an improvement in the skin manifestations of psoriasis in subjects with PsA.

Treatment with TREMFYA resulted in improvement in dactylitis and enthesitis in subjects with pre-existing dactylitis or enthesitis.

Physical Function

TREMFYA treated subjects in the TREMFYA 100 mg q8w group in both trials PsA1 and PsA2 showed greater mean improvement from baseline in physical function compared to subjects treated with placebo as assessed by the Health Assessment Questionnaire-Disability Index (HAQ-DI) at Weeks 16 and 24. In both trials, the proportion of HAQ-DI responders (≥0.35 improvement in HAQ-DI score) was greater in the TREMFYA q8w dose group compared to placebo at Weeks 16 and 24.

Other Health-Related Outcomes

General health status was assessed by the Short Form health survey (SF-36). At Week 24, subjects in the TREMFYA 100 mg q8w dose group in both trials PsA1 and PsA2 showed greater improvement from baseline in the SF-36 physical component summary (PCS) compared with placebo. There was not a statistically significant improvement observed in the SF-36 MCS. At Week 24, there was numerical improvement in the physical functioning, role-physical, bodily-pain, general health, social-functioning and vitality domains but not in the role-emotional and mental health domains. Fatigue was assessed by the Functional Assessment of Chronic Illness Therapy-Fatigue score (FACIT-F) in trials PsA1 and PsA2. Treatment with TREMFYA resulted in improvement in fatigue as measured by FACIT-F.

14.3 Clinical Studies in Adults with Ulcerative Colitis

The efficacy and safety of TREMFYA was assessed in three randomized, double-blind, placebo-controlled trials (UC1, UC2, and UC 4) that enrolled adult subjects with moderately to severely active ulcerative colitis. Disease activity was assessed by the modified Mayo score (mMS), a 3-component Mayo score (0 –9) which consists of the following subscores (0 to 3 for each subscore): stool frequency (SFS), rectal bleeding (RBS), and findings on centrally reviewed endoscopy (ES). An ES of 2 was defined by marked erythema, lack of vascular pattern, friability, and/or erosions; an ES of 3 was defined by spontaneous bleeding and ulceration. Enrolled subjects with a mMS between 5 and 9 and an ES of 2 or 3 were classified as having moderately to severely active ulcerative colitis. Subjects with inadequate response, loss of response, or intolerance to corticosteroids, immunomodulators (azathioprine, 6-mercaptopurine), biologic therapy (TNF blockers, vedolizumab), and/or Janus kinase (JAK) inhibitors were enrolled. In UC4, subjects with inadequate response, loss of response, or intolerance to sphingosine-1-phosphate receptor modulators (S1PRM) were also enrolled.

Induction Trial: UC1

In the 12-week induction trial (UC1; NCT04033445), 701 adult subjects with moderately to severely active ulcerative colitis were randomized 3:2 to receive either TREMFYA 200 mg or placebo by intravenous infusion at Week 0, Week 4, and Week 8.

At baseline in trial UC1, the median mMS was 7, 64% of subjects had severely active disease (mMS ≥7), and 68% of subjects had an ES of 3. In trial UC1, 49% of subjects had previously failed (inadequate response, loss of response, or intolerance) treatment with at least one biologic therapy and/or JAK inhibitor, 48% were biologic and JAK inhibitor naïve, and 3% had previously received but not failed a biologic or JAK inhibitor. The median age was 39 years (ranging from 18 to 79 years); 43% were female; and 72% identified as White, 21% as Asian, 1% as Black or African American, <1% as American Indian or Alaskan Native, and <1% as multiple racial groups.

Enrolled subjects were permitted to use stable doses of oral aminosalicylates, immunomodulators (azathioprine, 6-mercaptopurine, methotrexate), and/or oral corticosteroids (up to 20 mg/day prednisone or equivalent). At baseline, 72% of subjects were receiving aminosalicylates, 21% of subjects were receiving immunomodulators, and 43% of subjects were receiving corticosteroids. Concomitant biologic therapies or JAK inhibitors were not permitted.

In trial UC1, the primary endpoint was clinical remission at Week 12 as defined by the mMS. Secondary endpoints at Week 12 included endoscopic improvement, clinical response, and histologic endoscopic mucosal improvement (see Table 11).

Table 11: Proportion of Adult Subjects with Moderately to Severely Active Ulcerative Colitis Meeting Efficacy Endpoints at Week 12 in Trial UC1
Endpoint | Placebo | TREMFYA 200 mg Intravenous Infusion [TREMFYA 200 mg as an intravenous infusion at Week 0, Week 4, and Week 8] | Treatment Difference (95% CI)
Clinical remission [A stool frequency subscore of 0 or 1 and not increased from baseline, a rectal bleeding subscore of 0, and an endoscopy subscore of 0 or 1 with no friability]
Total Population | N=280 8% | N=421 23% | 15% (10%, 20%) [p <0.001, adjusted treatment difference (95% CI) based on Cochran-Mantel-Haenszel method (adjusted for stratification factors: biologic and/or JAK-inhibitor failure status and concomitant use of corticosteroids at baseline)]
Prior biologic and/or JAK inhibitor failure [Includes inadequate response, loss of response, or intolerance to biologic therapy (TNF blockers, vedolizumab) and/or a Janus kinase (JAK) inhibitor for ulcerative colitis] | N=136 4% | N=208 13%
Without prior biologic or JAK inhibitor failure [Includes subjects that were biologic and/or JAK inhibitor naïve and subjects with biologic and/or JAK inhibitor exposure who did not meet criteria for failure. Of these, 7 subjects in the placebo group and 11 subjects in the TREMFYA group were previously exposed to, but did not fail, a biologic or JAK inhibitor] | N=144 12% | N=213 32%
Endoscopic improvement [An endoscopy subscore of 0 or 1 with no friability]
Total Population | N=280 11% | N=421 27% | 16% (10%, 21%)
Prior biologic and/or JAK inhibitor failure | N=136 5% | N=208 15%
Without prior biologic or JAK inhibitor failure | N=144 17% | N=213 38%
Clinical response [Decrease from induction baseline in the modified Mayo score by ≥30% and ≥2 points, with either a ≥1 point decrease from baseline in the rectal bleeding subscore or a rectal bleeding subscore of 0 or 1]
Total Population | N=280 28% | N=421 62% | 34% (27%, 41%)
Prior biologic and/or JAK inhibitor failure | N=136 20% | N=208 51%
Without prior biologic or JAK inhibitor failure | N=144 35% | N=213 71%
Histologic endoscopic mucosal improvement (HEMI) [An endoscopy subscore of 0 or 1 with no friability and Geboes score ≤3.1 (indicating neutrophil infiltration in <5% of crypts, no crypt destruction, and no erosions, ulcerations, or granulation tissue)]
Total Population | N=280 8% | N=421 24% | 16% (11%, 21%)
Prior biologic and/or JAK inhibitor failure | N=136 4% | N=208 13%
Without prior biologic or JAK inhibitor failure | N=144 10% | N=213 33%

Trial UC1 was not designed to evaluate the relationship of histologic endoscopic mucosal improvement at Week 12 to disease progression and long-term outcomes.

Rectal Bleeding and Stool Frequency Subscores

Decreases in rectal bleeding and stool frequency subscores were observed as early as Week 4 in subjects treated with intravenous TREMFYA compared to placebo.

Endoscopic Assessment

Normalization of the endoscopic appearance of the mucosa (endoscopic remission) was defined as ES of 0. At Week 12 of UC1, a greater proportion of subjects treated with TREMFYA compared to placebo-treated subjects achieved endoscopic remission (15% vs 5%).

Fatigue Response

In trial UC1, subjects treated with TREMFYA experienced a clinically meaningful improvement in fatigue, assessed by the PROMIS-Fatigue Short form 7a, at Week 12, compared to placebo-treated subjects. The effect of TREMFYA to improve fatigue after 12 weeks of induction has not been established.

Maintenance Trial: UC2

The maintenance trial (UC2) evaluated 568 subjects who received one of two intravenous TREMFYA induction regimens, including the recommended 200 mg regimen, for 12 weeks in trials UC1 or UC3 (induction dose-finding study) and demonstrated clinical response per mMS after 12 weeks. Subjects were re-randomized to receive a subcutaneous maintenance regimen of either TREMFYA 100 mg every 8 weeks, TREMFYA 200 mg every 4 weeks, or placebo for up to an additional 44 weeks.

In trial UC2, 42% of subjects had failed (inadequate response, loss of response, or intolerance) treatment with one or more biologics or JAK inhibitors.

The primary endpoint was clinical remission at Week 44 defined by mMS. Secondary endpoints included corticosteroid-free clinical remission, endoscopic improvement, histologic endoscopic mucosal improvement, all at Week 44 and maintenance of clinical remission at Week 44 in subjects who achieved clinical remission 12 weeks after intravenous TREMFYA induction treatment (see Table 12).

Table 12: Proportion of Adult Subjects with Moderately to Severely Active Ulcerative Colitis Meeting Efficacy Endpoints at Week 44 in Trial UC2
Endpoint | Placebo | TREMFYA 100 mg Every 8 Weeks Subcutaneous Injection [TREMFYA 100 mg as a subcutaneous injection every 8 weeks after the induction regimen] | TREMFYA 200 mg Every 4 Weeks Subcutaneous Injection [TREMFYA 200 mg as a subcutaneous injection every 4 weeks after the induction regimen] | Treatment Difference vs Placebo (95% CI)
Endpoint | Placebo | TREMFYA 100 mg Every 8 Weeks Subcutaneous Injection [TREMFYA 100 mg as a subcutaneous injection every 8 weeks after the induction regimen] | TREMFYA 200 mg Every 4 Weeks Subcutaneous Injection [TREMFYA 200 mg as a subcutaneous injection every 4 weeks after the induction regimen] | TREMFYA 100 mg | TREMFYA 200 mg
Clinical remission [A stool frequency subscore of 0 or 1 and not increased from induction baseline, a rectal bleeding subscore of 0, and an endoscopy subscore of 0 or 1 with no friability]
Total population [Subjects who achieved clinical response 12 weeks following the intravenous administration of TREMFYA in either induction trial UC1 or induction dose-finding trial UC4] | N=190 19% | N=188 45% | N=190 50% | 25% (16%, 34%) [p <0.001, adjusted treatment difference (95% CI) based on Cochran-Mantel-Haenszel method adjusted for randomization stratification factors] | 30% (21%, 38%)
Prior biologic and/or JAK inhibitor failure [Includes inadequate response, loss of response, or intolerance to biologic therapy (TNF blockers, vedolizumab) and/or a Janus kinase (JAK) inhibitor for ulcerative colitis] | N=75 8% | N=77 40% | N=88 40%
Without prior biologic or JAK inhibitor failure [Includes subjects that were biologic and/or JAK inhibitor naïve and subjects with biologic and/or JAK inhibitor exposure who did not meet criteria for failure. Of these, 7 subjects in the placebo group, 6 subjects in the TREMFYA 100 mg group, and 6 subjects in the TREMFYA 200 mg group were previously exposed to, but did not fail, a biologic or JAK inhibitor] | N=115 26% | N=111 49% | N=102 59%
Corticosteroid-free clinical remission [Not requiring any treatment with corticosteroids for at least 8 weeks prior to week 44 and also meeting the criteria for clinical remission at week 44]
Total population | N=190 18% | N=188 45% | N=190 49% | 26% (17%, 34%) | 29% (20%, 38%)
Prior biologic and/or JAK inhibitor failure | N=75 7% | N=77 40% | N=88 40%
Without prior biologic or JAK inhibitor failure | N=115 26% | N=111 49% | N=102 57%
Endoscopic improvement [An endoscopy subscore of 0 or 1 with no friability]
Total population | N=190 19% | N=188 49% | N=190 52% | 30% (21%, 38%) | 31% (22%, 40%)
Prior biologic and/or JAK inhibitor failure | N=75 8% | N=77 45% | N=88 42%
Without prior biologic or JAK inhibitor failure | N=115 26% | N=111 52% | N=102 60%
Histologic endoscopic mucosal improvement (HEMI) [An endoscopy subscore of 0 or 1 with no friability and Geboes score ≤3.1 (indicating neutrophil infiltration in <5% of crypts, no crypt destruction, and no erosions, ulcerations, or granulation tissue)]
Total population | N=190 17% | N=188 44% | N=190 48% | 26% (17%, 34%) | 30% (21%, 38%)
Prior biologic and/or JAK inhibitor failure | N=75 8% | N=77 38% | N=88 39%
Without prior biologic or JAK inhibitor failure | N=115 23% | N=111 48% | N=102 56%
Maintenance of Clinical Remission at Week 44 in subjects who achieved clinical remission after 12 weeks of induction
Total population [Subjects who achieved clinical remission 12 weeks following intravenous administration of TREMFYA in either induction trial UC1 or induction dose-finding trial UC4] | N=59 34% | N=66 61% | N=69 72% | 26% (9%, 43%) [p <0.01, adjusted treatment difference (95% CI) based on Cochran-Mantel-Haenszel method adjusted for randomization stratification factors] | 38% (23%, 54%)
Prior biologic and/or JAK inhibitor failure | N=15 27% | N=20 60% | N=18 56%
Without prior biologic or JAK inhibitor failure [Includes subjects that were biologic and/or JAK inhibitor naïve and subjects with biologic and/or JAK inhibitor exposure who did not meet criteria for failure. Of these, 3 subjects in the placebo group, 3 subjects in the TREMFYA 100 mg group, and 3 subjects in the TREMFYA 200 mg group were previously exposed to, but did not fail, a biologic or JAK inhibitor.] | N=44 36% | N=46 61% | N=51 78%

Trial UC2 was not designed to evaluate the relationship of histologic endoscopic mucosal improvement at Week 44 to disease progression and long-term outcomes.

Endoscopic Assessment

Normalization of the endoscopic appearance of the mucosa (endoscopic remission) was defined as ES of 0. In UC2, greater proportions of subjects treated with TREMFYA 100 mg every 8 weeks or TREMFYA 200 mg every 4 weeks achieved endoscopic remission at Week 44 compared to placebo-treated subjects (35% and 34%, respectively, vs. 15%).

Trial UC4

In trial UC4 (NCT05528510), subjects with moderately to severely active ulcerative colitis were randomized 1:1:1 to receive TREMFYA 400 mg subcutaneous induction at Weeks 0, 4, and 8 followed by TREMFYA 200 mg subcutaneous maintenance every 4 weeks beginning at Week 12; TREMFYA 400 mg subcutaneous induction at Weeks 0, 4, and 8 followed by TREMFYA 100 mg subcutaneous maintenance every 8 weeks beginning at Week 16; or placebo. Efficacy was evaluated in 395 randomized subjects.

At baseline in trial UC4, the median mMS was 7; 65% of subjects had severely active disease (mMS ≥7), and 59% of subjects had an ES of 3. A total of 41% of subjects had previously failed treatment with at least one biologic therapy, JAK inhibitor, and/or S1PRM, 57% were biologic, JAK inhibitor, and S1PRM naïve, and 2% had previously received but had not failed a biologic, JAK inhibitor, or S1PRM. The median age of subjects was 40 years (ranging from 18 to 80 years); 39% were female; and 64% identified as White, 30% as Asian, and 3% as Black or African American.

Enrolled subjects were permitted to use stable doses of oral aminosalicylates, immunomodulators (azathioprine, 6-mercaptopurine, methotrexate), and/or oral corticosteroids (up to 20 mg/day prednisone or equivalent). At baseline, 78% of subjects were receiving aminosalicylates, 21% of subjects were receiving immunomodulators, and 33% of subjects were receiving corticosteroids. Concomitant biologic therapies, JAK inhibitors, or S1PRMs were not permitted.

In trial UC4, the primary endpoint was clinical remission at Week 12 as defined by the mMS. Secondary endpoints at Week 12 included endoscopic improvement, clinical response, and histologic-endoscopic mucosal improvement. Secondary endpoints at Week 24 included clinical remission and endoscopic improvement. The results of analyses of multiplicity-controlled efficacy endpoints in trial UC4 are shown in Table 13.

Table 13: Proportion of Adult Subjects with Moderately to Severely Active Ulcerative Colitis Meeting Efficacy Endpoints at Week 12 and Week 24 in Trial UC 4
Endpoint | Placebo | TREMFYA 400 mg Subcutaneous Injection at Weeks 0, 4, and 8 [At baseline, subjects were randomized 1:1:1 to receive subcutaneous TREMFYA 400 mg at Weeks 0, 4, and 8 followed by subcutaneous TREMFYA 100 mg every 8 weeks; subcutaneous TREMFYA 400 mg at Weeks 0, 4, and 8 followed by subcutaneous TREMFYA 200 mg every 4 weeks; or placebo. Because dosing is identical through Week 12, subjects in both TREMFYA groups are combined for the analysis of the Week 12 endpoints] |  | Treatment Difference vs Placebo (95% CI) [The adjusted treatment difference and the CIs were based on the common risk difference calculated using Mantel-Haenszel stratum weights and Sato variance estimator. The stratification variables used were prior biologic, JAK inhibitor, and/or S1PRM failure status (Yes or No), and Mayo endoscopy subscore at baseline (moderate [2] or severe [3]).]
Week 12
Clinical remission [A stool frequency subscore of 0 or 1 and not increased from induction baseline, a rectal bleeding subscore of 0, and an endoscopy subscore of 0 or 1 with no friability]
Total Population | N=130 7% | N=265 26% |  | 19% (12%, 26%) [p <0.001]
Prior biologic, JAK inhibitor, and/or S1PRM failure [Includes inadequate response, loss of response, or intolerance to biologic therapy (TNF blockers, vedolizumab), a Janus kinase (JAK) inhibitor, and/or S1PRM for ulcerative colitis] | N=55 4% | N=107 14%
Without prior biologic, JAK inhibitor, or S1PRM failure [Includes subjects that were biologic, JAK inhibitor, and S1PRM naïve and subjects with biologic, JAK inhibitor, and/or S1PRM exposure, who did not meet criteria for failure. Of these, 3 subjects in the placebo group and 3 subjects in the TREMFYA group were previously exposed to, but did not fail, a biologic, JAK inhibitor, or S1PRM] | N=75 9% | N=158 35%
Endoscopic improvement [An endoscopy subscore of 0 or 1 with no friability]
Total Population | N=130 12% | N=265 36% |  | 24% (17%, 32%)
Prior biologic, JAK inhibitor, and/or S1PRM failure | N=55 5% | N=107 22%
Without prior biologic, JAK inhibitor, or S1PRM failure | N=75 16% | N=158 46%
Clinical response [Decrease from baseline in the modified Mayo score by ≥30% and ≥2 points, with either a ≥1 point decrease from baseline in the rectal bleeding subscore or a rectal bleeding subscore of 0 or 1]
Total population | N=130 35% | N=265 66% |  | 30% (21%, 40%)
Prior biologic, JAK inhibitor, and/or S1PRM failure | N=55 25% | N=107 56%
Without prior biologic, JAK inhibitor, or S1PRM failure | N=75 43% | N=158 73%
Histologic endoscopic mucosal improvement [An endoscopy subscore of 0 or 1 with no friability and Geboes score ≤3.1 (indicating neutrophil infiltration in <5% of crypts, no crypt destruction, and no erosions, ulcerations, or granulation tissue)]
Total Population | N=130 10% | N=265 30% |  | 20% (13%, 27%)
Prior biologic, JAK inhibitor, and/or S1PRM failure | N=55 5% | N=107 19%
Without prior biologic, JAK inhibitor, or S1PRM failure | N=75 13% | N=158 38%
Week 24
Endpoint | Placebo | TREMFYA 100 mg Subcutaneous Injection every 8 weeks starting at Week 16 | TREMFYA 200 mg Subcutaneous Injection every 4 weeks starting at Week 12 | Treatment difference vs Placebo (95% CI)
Endpoint | Placebo | TREMFYA 100 mg Subcutaneous Injection every 8 weeks starting at Week 16 | TREMFYA 200 mg Subcutaneous Injection every 4 weeks starting at Week 12 | TREMFYA 100 mg | TREMFYA 200 mg
Clinical remission
Total Population | N=130 10% | N=134 34% | N=131 34% | 23% (14%, 33%) | 24% (15%, 34%)
Prior biologic, JAK inhibitor, and/or S1PRM failure | N=55 5% | N=55 13% | N=52 25%
Without prior biologic, JAK inhibitor, or S1PRM failure | N=75 13% | N=79 48% | N=79 41%
Endoscopic improvement
Total Population | N=130 12% | N=134 39% | N=131 44% | 27% (17%, 37%) | 32% (22%, 41%)
Prior biologic, JAK inhibitor, and/or S1PRM failure | N=55 5% | N=55 16% | N=52 35%
Without prior biologic, JAK inhibitor, or S1PRM failure | N=75 16% | N=79 54% | N=79 49%

Rectal Bleeding and Stool Frequency Subscores

Decreases in rectal bleeding and stool frequency subscores were observed as early as Week 3 in subjects treated with subcutaneous TREMFYA compared to placebo.

Endoscopic Assessment

Normalization of the endoscopic appearance of the mucosa (endoscopic remission) was defined as ES of 0. At Week 12 of UC4, a greater proportion of subjects treated with TREMFYA compared to placebo-treated subjects achieved endoscopic remission (16% vs 2%). Greater proportions of subjects treated with TREMFYA 100 mg every 8 weeks or TREMFYA 200 mg every 4 weeks achieved endoscopic remission at Week 24 compared to placebo-treated subjects (20% and 27%, respectively, vs 3%).

14.4 Clinical Studies in Adults with Crohn's Disease

The efficacy and safety of TREMFYA were assessed in three randomized, double-blind, placebo-controlled trials that enrolled adult subjects with moderately to severely active Crohn's disease who had a history of inadequate response, loss of response, or intolerance to oral corticosteroids, immunomodulators (azathioprine, 6-mercaptopurine, methotrexate), and/or biologic therapy (TNF blockers or vedolizumab). Moderately to severely active Crohn's disease was defined as a Crohn's Disease Activity Index (CDAI) score of ≥220 and a Simple Endoscopic Score for Crohn's Disease (SES-CD) of ≥6 (or ≥4 for subjects with isolated ileal disease). Subjects were permitted to use stable doses of oral corticosteroids (prednisone ≤40 mg/day or equivalent), immunomodulators (azathioprine, 6-mercaptopurine, methotrexate), and/or aminosalicylates.

Trials CD1 and CD2

In trial CD1 (NCT03466411), 361 subjects were randomized to receive intravenous TREMFYA 200 mg at Weeks 0, 4, and 8 (N = 285) or placebo (N = 76). The median age of subjects enrolled into trial CD1 was 33 years (range: 18 – 83 years); 46% were female; and 75% identified as White, 22% as Asian, 1% as Black or African American, <1% as Native Hawaiian or Pacific Islander, and 2% did not report their racial group. The median baseline CDAI score was 285 (range: 220 – 442), and the median baseline SES-CD score was 11 (range: 4 – 39). Of the randomized subjects, 52% of subjects had previously failed (inadequate response, loss of response, or intolerance) treatment with at least one biologic therapy, 43% were biologic-naïve, and 6% had previously received but had not failed a biologic. At baseline, 37% of subjects were receiving oral corticosteroids and 30% of subjects were receiving immunomodulators (azathioprine, 6-mercaptopurine, methotrexate).

In trial CD2 (NCT03466411), 360 subjects were randomized to receive intravenous TREMFYA 200 mg at Weeks 0, 4, and 8 (N = 288) or placebo (N = 72). The median age of subjects enrolled into trial CD2 was 33 years (range:18 – 72 years); 39% were female; and 73% identified as White, 23% as Asian, 1% as Black or African American, <1% as Native Hawaiian or Pacific Islander, and 2% did not report their racial group. The median baseline CDAI score was 286 (range: 220 – 442) and the median baseline SES-CD score was 11 (range: 4 – 42). Of the randomized subjects, 52% of subjects had previously failed (inadequate response, loss of response, or intolerance) treatment with at least one biologic therapy, 41% were biologic-naïve, and 7% had previously received but had not failed a biologic. At baseline, 36% of the subjects were receiving oral corticosteroids and 31% of the subjects were receiving immunomodulators (azathioprine, 6-mercaptopurine, methotrexate).

The results of efficacy endpoints at Week 12 for CD1 and CD2 trials are shown in Table 14.

Table 14: Proportion of Adult Subjects with Moderately to Severely Active Crohn’s Disease Meeting Efficacy Endpoints at Week 12 in Trials CD1 and CD2
 | Trial CD1 |  |  | Trial CD2
Endpoint | Placebo | TREMFYA 200 mg Intravenous Infusion [TREMFYA 200 mg as an intravenous infusion at Weeks 0, 4, and 8.] | Treatment Difference vs Placebo (95% CI) [The adjusted treatment difference and the confidence intervals (CIs) were based on the common risk difference test using Mantel-Haenszel stratum weights and the Sato variance estimator. The stratification variables used were baseline CDAI score (≤300 or >300), baseline SES-CD score (≤12 or >12), BIO-Failure status (Yes or No), and baseline corticosteroid use (Yes or No).] | Placebo | TREMFYA 200 mg Intravenous Infusion | Treatment Difference vs Placebo (95% CI)
Clinical remission [Clinical remission is defined as CDAI score <150.] at Week 12
Total population | N=76 20% | N=285 47% | 27% (17%, 38%) [p <0.001] | N=72 15% | N=288 47% | 31% (21%, 41%)
Prior biologic failure [Includes inadequate response, loss of response, or intolerance to biologic therapy (TNF blockers, vedolizumab) for Crohn's disease.] | N=39 21% | N=147 44% |  | N=39 15% | N=148 47%
Without prior biologic failure [Includes subjects that were biologic naïve and subjects with prior biologic exposure who did not meet criteria for failure. In CD1, 3 subjects in the placebo group and 18 subjects in the intravenous TREMFYA 200 mg group were previously exposed to but did not fail a biologic therapy. In CD2, 6 subjects in the placebo group and 19 subjects in the intravenous TREMFYA 200 mg group were previously exposed to but did not fail a biologic therapy.] | N=37 19% | N=138 49% |  | N=33 15% | N=140 48%
Endoscopic response [Endoscopic response is defined as >50% improvement from baseline in SES-CD score.] at Week 12
Total population | N=76 9% | N=285 36% | 27% (19%, 35%) | N=72 13% | N=288 34% | 21% (11%, 30%)
Prior biologic failure | N=39 3% | N=147 26% |  | N=39 8% | N=148 28%
Without prior biologic failure | N=37 16% | N=138 47% |  | N=33 18% | N=140 40%
Clinical remissionat Week 12 and endoscopic responseat Week 12
Total population | N=76 3% | N=285 20% | 17% (11%, 23%) | N=72 3% | N=288 21% | 18% (12%, 24%)
Prior biologic failure | N=39 3% | N=147 14% |  | N=39 3% | N=148 19%
Without prior biologic failure | N=37 3% | N=138 26% |  | N=33 3% | N=140 24%

Stool Frequency and Abdominal Pain

Greater reductions in stool frequency and abdominal pain were observed as early as Week 4 in subjects treated with intravenous TREMFYA compared to placebo.

Trial CD3

In trial CD3, 340 subjects were randomized in a 1:1:1 ratio to receive subcutaneous TREMFYA 400 mg at Weeks 0, 4, and 8 followed by subcutaneous TREMFYA 100 mg every 8 weeks (with the first dose given at Week 16); subcutaneous TREMFYA 400 mg at Weeks 0, 4, and 8 followed by subcutaneous TREMFYA 200 mg every 4 weeks (with the first dose given at Week 12); or placebo. The median age of subjects enrolled into trial CD3 was 36 years (range: 18 – 83 years); 41% were female; and 66% identified as White, 22% as Asian, 3% as Black or African American, and 9% did not report their racial group. The median baseline CDAI score was 291 (range: 220 – 447), and the median baseline SES-CD score was 10 (range: 4 – 40). Of the randomized subjects, 46% of subjects had previously failed (inadequate response, loss of response, or intolerance) treatment with at least one biologic therapy, 47% were biologic naïve, and 7% had previously received but had not failed a biologic. At baseline, 30% of the subjects were receiving oral corticosteroids and 29% of the subjects were receiving immunomodulators (azathioprine, 6-mercaptopurine, methotrexate).

In trial CD3, the coprimary endpoints were clinical remission at Week 12 and endoscopic response at Week 12 compared to placebo. Additional efficacy endpoints included clinical response at Week 12, clinical remission at Week 24, clinical remission at Week 48, and endoscopic response at Week 48. The results of analyses of multiplicity-controlled efficacy endpoints in trial CD3 are shown in Table 15.

Table 15: Proportion of Adult Subjects with Moderately to Severely Active Crohn's Disease Meeting Efficacy Endpoints in Trial CD3
Endpoint | Placebo | TREMFYA 400 mg Subcutaneous Injection at Weeks 0, 4, and 8 [At baseline, subjects were randomized 1:1:1 to receive subcutaneous TREMFYA 400 mg at Weeks 0, 4, and 8 followed by subcutaneous TREMFYA 100 mg every 8 weeks; subcutaneous TREMFYA 400 mg at Weeks 0, 4, and 8 followed by subcutaneous TREMFYA 200 mg every 4 weeks; or placebo. Because dosing is identical through Week 12, subjects in both TREMFYA groups are combined for the analysis of the Week 12 endpoints.] |  | Treatment Difference vs Placebo (95% CI) [The adjusted treatment difference and the CIs were based on the common risk difference test using Mantel-Haenszel stratum weights and the Sato variance estimator. The stratification variables used were baseline CDAI score (≤300 or >300), baseline SES-CD score (≤12 or >12), BIO-Failure status (Yes or No). CI = confidence interval]
Week 12
Clinical Remission [Clinical remission is defined as CDAI score <150.]
Total population | N=115 22% | N=225 56% |  | 34% (24%, 44%) [p<0.001]
Prior biologic failure [Includes inadequate response, loss of response, or intolerance to biologic therapy (TNF blockers, vedolizumab) for Crohn's disease.] | N=53 17% | N=104 60%
Without prior biologic failure [Includes subjects that were biologic naïve and subjects with prior biologic exposure who did not meet criteria for failure. Of these, 8 subjects in the placebo group and 17 subjects in the subcutaneous TREMFYA 400 mg group, were previously exposed to but did not fail a biologic therapy.] | N=62 26% | N=121 52%
Endoscopic Response [Endoscopic response is defined as >50% improvement from baseline in SES-CD score.]
Total population | N=115 15% | N=225 34% |  | 19% (10%, 28%)
Prior biologic failure | N=53 11% | N=104 27%
Without prior biologic failure | N=62 18% | N=121 40%
Clinical Response [Clinical response is defined as ≥100-point decrease from baseline in CDAI total score.]
Total population | N=115 33% | N=225 72% |  | 39% (29%, 50%)
Prior biologic failure | N=53 28% | N=104 76%
Without prior biologic failure | N=62 37% | N=121 69%
Weeks 24 and 48
Endpoint | Placebo | TREMFYA 100 mg Subcutaneous Injection every 8 weeks starting at Week 16 | TREMFYA 200 mg Subcutaneous Injection every 4 weeks starting at Week 12 | Treatment difference vs Placebo (95% CI)
Endpoint | Placebo | TREMFYA 100 mg Subcutaneous Injection every 8 weeks starting at Week 16 | TREMFYA 200 mg Subcutaneous Injection every 4 weeks starting at Week 12 | TREMFYA 100 mg | TREMFYA 200 mg
Clinical Remissionat Week 24
Total population | N=115 21% | N=114 61% | N=111 58% | 39% (28%, 51%) | 37% (25%, 48%)
Prior biologic failure | N=53 19% | N=54 63% | N=50 52%
Without prior biologic failure [Includes subjects that were biologic naïve and subjects with prior biologic exposure who did not meet criteria for failure. Of these, 8 subjects in the placebo group, 7 subjects in the subcutaneous TREMFYA 100 mg group, and 10 subjects in the subcutaneous TREMFYA 200 mg group were previously exposed to but did not fail a biologic therapy.] | N=62 23% | N=60 58% | N=61 62%
Clinical Remissionat Week 48
Total population | N=115 17% | N=114 59% | N=111 65% | 41% (30%, 52%) | 47% (36%, 58%)
Prior biologic failure | N=53 9% | N=54 56% | N=50 60%
Without prior biologic failure | N=62 24% | N=60 62% | N=61 69%
Endoscopic Responseat Week 48
Total population | N=115 5% | N=114 39% | N=111 48% | 34% (24%, 44%) | 42% (32%, 53%)
Prior biologic failure | N=53 0% | N=54 33% | N=50 52%
Without prior biologic failure | N=62 10% | N=60 45% | N=61 44%

Stool Frequency and Abdominal Pain

Greater reductions in stool frequency and abdominal pain were observed as early as Week 4 in subjects treated with subcutaneous TREMFYA 400 mg compared to placebo.

Endoscopic Remission at Week 48

Endoscopic remission was defined as an SES-CD score ≤4 and at least a 2-point reduction from baseline and no subscore greater than 1 in any individual component. In trial CD3, a greater proportion of subjects treated with either TREMFYA regimen (i.e., subcutaneous TREMFYA 400 mg at Weeks 0, 4, and 8 followed by subcutaneous TREMFYA 100 mg at Week 16 and every 8 weeks thereafter or subcutaneous TREMFYA 400 mg at Weeks 0, 4, and 8 followed by subcutaneous TREMFYA 200 mg at Week 12 and every 4 weeks thereafter) achieved endoscopic remission, compared to placebo-treated subjects (31% and 40%, respectively, vs. 6%).

16 HOW SUPPLIED/STORAGE AND HANDLING

How Supplied

TREMFYA® (guselkumab) injection is a clear and colorless to light yellow solution supplied as follows:

Subcutaneous Injection

- Carton of one 100 mg/mL single-dose One-Press patient‑controlled injector (NDC: 57894-640-11)
- Carton of one 100 mg/mL single-dose prefilled pen (TREMFYA PEN) (NDC: 57894-640-06)
- Carton of one 200 mg/2 mL single-dose prefilled pen (TREMFYA PEN) (NDC: 57894-651-02)
- Induction Pack for Ulcerative Colitis or Crohn's Disease: Carton containing two 200 mg/2 mL single-dose prefilled pens (400 mg/4 mL total) (TREMFYA PEN) (NDC: 57894-651-04)
- Carton of one 100 mg/mL single-dose prefilled syringe with a 27G, half inch fixed needle assembled in a passive needle guard delivery system (NDC: 57894-640-01)
- Carton of one 200 mg/2 mL (100 mg/mL) single-dose prefilled syringe with a 27G, half inch fixed needle assembled in a passive needle guard delivery system (NDC: 57894-651-22)

Intravenous Infusion

- Carton of one 200 mg/20 mL (10 mg/mL) single-dose vial (NDC: 57894-650-02)

Storage and Handling

TREMFYA is sterile and preservative-free. Discard any unused portion.

- Store in a refrigerator between 2 °C to 8 °C (36 °F to 46 °F).
- Store in original carton until time of use.
- Protect from light until use.
- Do not freeze.
- Do not shake.
- Not made with natural rubber latex.

17 PATIENT COUNSELING INFORMATION

Advise the patients and/or caregivers to read the FDA-approved patient labeling (Medication Guide and Instructions for Use) before starting TREMFYA therapy, and each time the prescription is renewed, as there may be new information they need to know.

Hypersensitivity Reactions

Advise patients to discontinue TREMFYA and seek immediate medical attention if they experience any symptoms of serious hypersensitivity reactions [see Warnings and Precautions (5.1)].

Infections

Instruct patients of the importance of communicating any history of infections to the healthcare provider and contacting their healthcare provider if they develop any symptoms of an infection [see Warnings and Precautions (5.2)].

Tuberculosis

Advise patients to contact their healthcare provider if they experience symptoms suggestive of TB (e.g., unexplained fever, cough, or difficulty breathing) [see Warnings and Precautions (5.3)].

Hepatotoxicity

Inform patients that TREMFYA may cause liver injury. Instruct patients to seek immediate medical attention if they experience symptoms suggestive of liver dysfunction (e.g., unexplained rash, nausea, vomiting, abdominal pain, fatigue, anorexia, or jaundice and/or dark urine) [see Warnings and Precautions (5.4)].

Immunizations

Advise patients treated with TREMFYA to avoid use of live vaccines [see Warnings and Precautions (5.5)].

Ulcerative Colitis and Crohn's Disease Subcutaneous Induction Dosing Instructions (400 mg Subcutaneous dose)

If patients are to receive the 400 mg subcutaneous induction dosage for ulcerative colitis or Crohn's disease, instruct patients or caregivers to administer two 200 mg prefilled pens or prefilled syringes to achieve the full 400 mg dose [see Medication Guide and Instructions for Use].

Instruction on Injection Technique

Instruct patients or caregivers to perform the first self-injection under the supervision and guidance of a qualified healthcare professional for proper training in subcutaneous injection technique, including injection of the full dose [see Medication Guide and Instructions for Use].

Proper Sharps Disposal Instructions

Counsel patients and caregivers on the proper technique of needle and syringe disposal. Instruct patients to dispose needles and syringes in a puncture-resistant container. Advise patients and caregivers not to reuse needles or syringes.

Administration Instructions

Instruct patients that if they forget to administer a dose of TREMFYA, then they should administer TREMFYA as soon as they remember. Instruct patients to administer the next dose at the regular scheduled time.

Pregnancy

Advise patients that there is a pregnancy registry that monitors pregnancy outcomes in patients exposed to TREMFYA during pregnancy [see Use in Specific Populations (8.1)].

Manufactured by:
Janssen Biotech, Inc.
Horsham, PA 19044, USA
U.S. License No. 1864

For patent information: www.janssenpatents.com
© Johnson & Johnson and its affiliates 2017–2025

Medication Guide

TREMFYA® (trem fye´ ah)
(guselkumab)
injection, for subcutaneous or intravenous use

What is the most important information I should know about TREMFYA?
TREMFYA may cause serious side effects, including:

- Serious allergic reactions. Stop using TREMFYA and get emergency medical help right away if you develop any of the following symptoms of a serious allergic reaction:

- fainting, dizziness, feeling lightheaded (low blood pressure)
- swelling of your face, eyelids, lips, mouth, tongue or throat

- trouble breathing or throat tightness
- chest tightness
- skin rash, hives
- itching

- Infections. TREMFYA is a medicine that may lower the ability of your immune system to fight infections and may increase your risk of infections. Your healthcare provider should check you for infections and tuberculosis (TB) before starting treatment with TREMFYA and may treat you for TB before you begin treatment with TREMFYA if you have a history of TB or have active TB. Your healthcare provider should watch you closely for signs and symptoms of TB during and after treatment with TREMFYA.
  Tell your healthcare provider right away if you have an infection or have symptoms of an infection, including:

- fever, sweats, or chills
- cough
- shortness of breath
- blood in your phlegm (mucus)

- muscle aches
- warm, red, or painful skin or sores on your body different from your psoriasis

- weight loss
- diarrhea or stomach pain
- burning when you urinate or urinating more often than normal

- Liver problems. With the treatment of Crohn's disease or ulcerative colitis, your healthcare provider will do blood tests to check your liver before and during treatment with TREMFYA. With the treatment of plaque psoriasis or psoriatic arthritis, your healthcare provider may do blood tests to check your liver before and as necessary during treatment with TREMFYA. Your healthcare provider may stop treatment with TREMFYA if you develop liver problems. Tell your healthcare provider right away if you notice any of the following symptoms:

- unexplained rash
- vomiting
- tiredness (fatigue)
- yellowing of the skin or the whites of your eyes

- nausea
- stomach pain (abdominal)
- loss of appetite
- dark urine

See "What are the possible side effects of TREMFYA?" for more information about side effects.

What is TREMFYA?

TREMFYA is a prescription medicine used to treat:

- adults and children 6 years of age and older who also weigh at least 88 pounds (40 kg) with moderate-to-severe plaque psoriasis who may benefit from taking injections or pills (systemic therapy) or phototherapy (treatment using ultraviolet or UV light)
- adults and children 6 years of age and older who also weigh at least 88 pounds (40 kg) with active psoriatic arthritis (PsA)
- adults with moderately to severely active ulcerative colitis
- adults with moderately to severely active Crohn's disease

It is not known if TREMFYA is safe and effective in children under 18 years of age with ulcerative colitis or Crohn’s disease or in children under 6 years of age with plaque psoriasis or psoriatic arthritis.

Do not use TREMFYA if you have had a serious allergic reaction to guselkumab or any of the other ingredients in TREMFYA. See the end of this Medication Guide for a complete list of ingredients in TREMFYA.

Before using TREMFYA, tell your healthcare provider about all of your medical conditions, including if you:

- have any of the conditions or symptoms listed in the section "What is the most important information I should know about TREMFYA?"
- have an infection that does not go away or that keeps coming back.
- have TB or have been in close contact with someone with TB.
- have recently received or are scheduled to receive an immunization (vaccine). You should avoid receiving live vaccines during treatment with TREMFYA. Children should be brought up to date with all vaccines before starting TREMFYA.
- are pregnant or plan to become pregnant. It is not known if TREMFYA can harm your unborn baby.
  Pregnancy Registry: If you become pregnant during treatment with TREMFYA, talk to your healthcare provider about registering in the pregnancy exposure registry for TREMFYA. You can enroll in this registry by visiting www.mothertobaby.org/ongoing-study/tremfya-guselkumab, by calling 1-877-311-8972, or emailing MotherToBaby@health.ucsd.edu. The purpose of this registry is to collect information about the safety of TREMFYA during pregnancy.
- are breastfeeding or plan to breastfeed. It is not known if TREMFYA passes into your breast milk.

Tell your healthcare provider about all the medicines you take, including prescription and over-the-counter medicines, vitamins, and herbal supplements.

How should I use TREMFYA?

See the detailed "Instructions for Use" that comes with TREMFYA for information on how to prepare and inject a dose of TREMFYA, and how to properly throw away (dispose of) the used TREMFYA prefilled syringe, One-Press injector or prefilled pen (TREMFYA PEN).

- Use TREMFYA exactly as your healthcare provider tells you to use it.
- If you miss your TREMFYA dose, inject a dose as soon as you remember. Then, take your next dose at your regular scheduled time. Call your healthcare provider if you are not sure what to do.
- If you inject more TREMFYA than prescribed, call your healthcare provider right away.
- Adults or children 6 years of age or older who also weigh at least 88 pounds (40 kg) with plaque psoriasis or psoriatic arthritis will receive TREMFYA as an injection under the skin (subcutaneous injection).
- Adults may self-inject with the TREMFYA prefilled pen, prefilled syringe, or One-Press injector.
- Adults with ulcerative colitis or Crohn’s disease will receive their beginning (induction) doses with TREMFYA through a vein in the arm (intravenous infusion) in a healthcare facility by a healthcare provider or as injections under the skin (subcutaneous injection). After completing the beginning (induction) doses, patients will receive TREMFYA as an injection under the skin (subcutaneous injection).

How will my child receive TREMFYA?
See the detailed "Instructions for Use" that comes with TREMFYA.

- Children with plaque psoriasis or psoriatic arthritis will receive TREMFYA as an injection under the skin (subcutaneous injection).
- Children should not self-inject using the TREMFYA prefilled syringe, One-Press injector, or Prefilled pen. A healthcare provider or caregiver should give children their injections.
- Your child's first dose will be given by a healthcare provider. If your child’s healthcare provider decides that you or another adult caregiver may give your child TREMFYA injections at home, you or the adult caregiver should be shown the right way to give the injections by your healthcare provider.

What are the possible side effects of TREMFYA?
TREMFYA may cause serious side effects including:

- See "What is the most important information I should know about TREMFYA?"

The most common side effects of TREMFYA include:

- respiratory tract infections
- joint pain (arthralgia)
- fungal skin infections
- bronchitis
- skin rash (rash)

- headache
- diarrhea
- herpes simplex infections
- feeling very tired (fatigue)

- injection site reactions
- stomach flu (gastroenteritis)
- stomach pain
- fever (pyrexia)

These are not all the possible side effects of TREMFYA. Call your doctor for medical advice about side effects. You may report side effects to FDA at 1-800-FDA-1088.

How should I store TREMFYA?

- Store TREMFYA in the refrigerator between 36 °F to 46 °F (2 °C to 8 °C).
- Keep TREMFYA in the original carton to protect it from light until time of use.
- TREMFYA is not made with natural rubber latex.
- Do not freeze TREMFYA.
- Do not shake TREMFYA.

Keep TREMFYA and all medicines out of the reach of children.

General information about the safe and effective use of TREMFYA.

Medicines are sometimes prescribed for purposes other than those listed in a Medication Guide. Do not use TREMFYA for a condition for which it was not prescribed. Do not give TREMFYA to other people, even if they have the same symptoms that you have. It may harm them. You can ask your healthcare provider or pharmacist for information about TREMFYA that is written for health professionals.

What are the ingredients in TREMFYA?
Active ingredient: guselkumab
Inactive ingredients: Single-dose prefilled syringe, single-dose One-Press patient-controlled injector, and single-dose prefilled pen (TREMFYA PEN) for subcutaneous use: L-histidine, L-histidine monohydrochloride monohydrate, polysorbate 80, sucrose and water for injection. Single-dose vial for intravenous infusion: EDTA disodium dihydrate, L-histidine, L-histidine monohydrochloride monohydrate, L-methionine, polysorbate 80, sucrose and water for injection.

Manufactured by: Janssen Biotech, Inc., Horsham, PA 19044, USA. U.S. License Number 1864
For patent information: www.janssenpatents.com
© Johnson & Johnson and its affiliates 2017–2025
For more information, call 1-800-526-7736 or go to www.tremfya.com.

This Medication Guide had been approved by the U.S. Food and Drug Administration.

Revised: 09/2025

INSTRUCTIONS FOR USE

TREMFYA® [trem fye' ah]
(guselkumab)
injection, for subcutaneous use
200 mg/2mL (100 mg/mL) Prefilled Syringe

This Instructions for Use contains information on how to inject TREMFYA.

SINGLE-DOSE

Important Information You Need to Know Before Injecting TREMFYA

TREMFYA comes in a single-dose prefilled syringe containing one 200 mg dose.

Your healthcare provider will tell you if you will need to use 1 or 2 prefilled syringes.

If your healthcare provider decides that you or a caregiver may be able to give your injections of TREMFYA at home, you should receive training on the correct way to prepare and inject TREMFYA before using the prefilled syringe.

Read this Instructions for Use before using your TREMFYA prefilled syringe and each time you get a refill. There may be new information. This leaflet does not take the place of talking with your healthcare provider about your medical condition or your treatment.

Each TREMFYA prefilled syringe can only be used one time. Throw the used prefilled syringe away (see Step 4) after one dose, even if there is still medicine left in it. Do not reuse your TREMFYA prefilled syringe.

The TREMFYA prefilled syringe is intended for injection under the skin, not into the muscle or vein. After injection, the needle will retract into the device and lock into place.

Storage information

Store in refrigerator between 36°F to 46°F (2°C to 8°C).

Do not freeze TREMFYA prefilled syringe.

Do not shake your TREMFYA prefilled syringe.

Keep TREMFYA prefilled syringe and all medicines out of reach of children.

Keep TREMFYA prefilled syringe in the original carton to protect from light and physical damage.

Prefilled syringe parts

1. Get ready

Check your dose to see if you will need to use 1 or 2 prefilled syringes and inspect carton(s)

Remove the carton(s) from the refrigerator.

Check the expiration ('EXP') date. Do not use your prefilled syringe if the expiration date has passed or if the seal on the carton is broken. Contact your healthcare provider or pharmacist for a new prefilled syringe.

Allow TREMFYA to come to room temperature

Let the cartons sit on a flat surface at room temperature for approximately 30 minutes before use.

Do not warm the prefilled syringe(s) any other way.

2. Prepare to inject TREMFYA

Take the prefilled syringe out of the carton.

Inspect liquid to see that it is clear and colorless to slightly yellow

Check the liquid in the viewing window. It should be clear and colorless to slightly yellow and may contain tiny white or clear particles. You may also see air bubbles. This is normal.

Do not inject if the liquid is:

- cloudy or
- discolored or
- has large particles

Do not use the prefilled syringe if it is dropped. Call your healthcare provider or pharmacist for a new prefilled syringe.

Choose injection site

Select a site from the following areas for your injection:

- Front of thighs
- Lower stomach area (lower abdomen), except for a 2-inch area right around your navel (belly-button)
- Back of upper arms (only if someone else is giving you the injection)

If you need to give 2 injections to complete your dose, choose different areas or leave at least 2 inches between injection sites.

Do not inject into skin that is tender, bruised, red, scaly, thick or hard. Avoid areas with scars or stretch marks.

Wash hands and clean injection site

Wash your hands well with soap and warm water.

Wipe your chosen injection site with an alcohol swab and allow it to dry.

Do not touch, fan, or blow on the injection site after you have cleaned it.

3. Inject TREMFYA

Remove needle cover when you are ready to inject

Hold the prefilled syringe by the body and pull needle cover straight off. It is normal to see a few drops of liquid.

Inject TREMFYA within 5 minutes of removing the needle cover.

Do not put needle cover back on, as this may damage the needle or cause a needle stick injury.

Do not touch needle or let it touch any surface.

Do not use the prefilled syringe if it is dropped. Call your healthcare provider or pharmacist for a new prefilled syringe.

Do not hold or pull the plunger at any time.

Pinch injection site and insert needle at about a 45-degree angle

It is important to pinch enough skin to inject under the skin and not into muscle.

Insert needle with a quick dart-like motion.

Slowly press plunger all the way down until it stops to inject all of the liquid

You will feel some resistance as you press the plunger, this is normal.

Release pressure from plunger to remove the needle from the skin

The needle will retract into the device and lock into place.

If your prescribed dose requires two injections, repeat Steps 2 to 4 with the second prefilled syringe.

4. After your injection

Check injection site

There may be a small amount of blood or liquid at the injection site. Gently hold pressure over the injection site with a cotton ball or gauze pad until any bleeding stops.

Do not rub the injection site.

If needed, cover the injection site with a bandage.

Dispose of your prefilled syringe

Put the used prefilled syringe in an FDA-cleared sharps disposal container right away after use.

Do not throw away (dispose of) your prefilled syringe in your household trash.

Do not recycle your used sharps disposal container.

For more information, see Disposing of TREMFYA prefilled syringe.

Disposing of TREMFYA prefilled syringe

If you do not have an FDA-cleared sharps disposal container, you may use a household container that is:

- made of heavy-duty plastic
- can be closed with a tight-fitting, puncture resistant lid, without sharps being able to come out
- upright and stable during use
- leak-resistant
- properly labeled to warn of hazardous waste inside the container

When your sharps disposal container is almost full, you will need to follow your community guidelines for the right way to dispose of your sharps disposal container. There may be state or local laws about how you should throw away used needles and syringes.

For more information about safe sharps disposal, and for specific information about sharps disposal in the state that you live in, go to the FDA's website at: www.fda.gov/safesharpsdisposal. You may also consult your pharmacist.

Need help?

Call your healthcare provider to talk about any questions you may have. For additional assistance or to share your feedback, call 800-526-7736.

Manufactured by:

Janssen Biotech, Inc.

Horsham, PA 19044, USA

US License No. 1864

This Instructions for Use has been approved by the U.S. Food and Drug Administration.

Approved: August / 2025

INSTRUCTIONS FOR USE

TREMFYA® PEN
[trem fye' ah Pen]
(guselkumab)
injection, for subcutaneous use
200 mg/2 mL Prefilled Pen

This Instructions for Use contains information on how to inject with TREMFYA PEN.

SINGLE-DOSE

Important Information You Need to Know Before Injecting with TREMFYA PEN

TREMFYA PEN comes in a single-dose Prefilled Pen containing one 200 mg dose.

Your healthcare provider will tell you if you will need to use 1 or 2 Prefilled Pens.

If your healthcare provider decides that you or a caregiver may be able to give your injections with TREMFYA PEN at home, you should receive training on the correct way to prepare and inject with TREMFYA PEN before using the Prefilled Pen.

Read this Instructions for Use before using your Prefilled Pen and each time you get a new Prefilled Pen. There may be new information. This leaflet does not take the place of talking with your healthcare provider about your medical condition or your treatment.

Each TREMFYA PEN can only be used one time. Throw the used Prefilled Pen away (see Step 4) after one dose, even if there is still medicine left in it. Do not reuse your Prefilled Pen.

Storage information

Store in refrigerator between 36°F to 46°F (2°C to 8°C).

Do not freeze your TREMFYA PEN.

Do not shake your TREMFYA PEN.

Keep your TREMFYA PEN and all medicines out of reach of children.

Keep your TREMFYA PEN in the original carton to protect from light and physical damage.

TREMFYA PEN parts

1. Get ready

Check your prescribed dose to see if you will need to use 1 or 2 Prefilled Pens and inspect carton(s)

Remove the carton(s) from the refrigerator.

Check the expiration ('EXP') date.

Do not use the Prefilled Pen if the expiration date has passed or if the seal on the carton is broken. Contact your healthcare provider or pharmacist for a new Prefilled Pen.

Allow TREMFYA PEN to come to room temperature

Let the carton(s) sit on a flat surface at room temperature for approximately 30 minutes before use.

Do not warm the Prefilled Pen(s) any other way.

2. Prepare to inject with TREMFYA PEN

Take your Prefilled Pen out of the carton.

Inspect liquid in window to see that it is clear and colorless to slightly yellow

Check the liquid in the viewing window. It should be clear and colorless to slightly yellow and may contain tiny white or clear particles. You may also see air bubbles. This is normal.

Do not inject if the liquid is:

- cloudy or
- discolored or
- has large particles

Call your healthcare provider or pharmacist for a new Prefilled Pen.

Choose injection site

Select from the following areas for your injection:

- Front of thighs
- Lower stomach area (lower abdomen), except for a 2-inch area right around your navel (belly-button)
- Back of upper arms (only if someone else is giving you the injection)

If you need to give 2 injections to complete your dose, choose different areas or leave at least 2 inches between injection sites.

Do not inject into skin that is tender, bruised, red, scaly, thick or hard. Avoid areas with scars or stretch marks.

Wash hands and clean injection site

Wash your hands well with soap and warm water.

Wipe your chosen injection site with an alcohol swab and allow it to dry.

Do not touch, fan, or blow on the injection site after you have cleaned it.

3. Inject with TREMFYA PEN

Remove cap when you are ready to inject

Do Not Touch Yellow Needle Guard!

This may start the injection and you will not receive the dose.

Pull the cap straight off. It is normal to see a few drops of liquid.

Inject with TREMFYA PEN within 5 minutes of removing cap.

Do not put the cap back on as this may damage the needle.

Do not use your Prefilled Pen if it is dropped after removing the cap. Call your healthcare provider or pharmacist for a new Prefilled Pen.

Position the Prefilled Pen straight onto the injection site then push and hold the Prefilled Pen

Do Not Lift The Prefilled Pen During Injection!

If you do, the yellow needle guard will lock and the full dose will not be delivered.

Position your Prefilled Pen straight onto the injection site with the yellow needle guard against the skin and the viewing window facing you.

Press down on the Prefilled Pen and keep holding it down against the skin.

You will hear the first click.

Keep holding your Prefilled Pen firmly against the skin for about 10 seconds to hear a second click

You are almost done.

Keep holding firmly against the skin and confirm your injection is complete

Your injection is complete when the plunger rod stops moving and fills the viewing window.

Lift straight up

If your prescribed dose requires two injections, repeat Steps 2 to 4 with the second Prefilled Pen.

4. After your injection

Check injection site

There may be a small amount of blood or liquid at the injection site. Gently hold pressure over the injection site with a cotton ball or gauze pad until any bleeding stops.

Do not rub the injection site. If needed, cover the injection site with a bandage.

Dispose of your Prefilled Pen and cap

Put your used Prefilled Pen and cap in an FDA-cleared sharps disposal container right away after use.

Do not throw away (dispose of) your Prefilled Pen in your household trash.

Do not recycle your used sharps disposal container.

For more information, see Disposing of TREMFYA PEN.

Disposing of TREMFYA PEN

If you do not have an FDA-cleared sharps disposal container, you may use a household container that is:

- made of heavy-duty plastic
- can be closed with a tight-fitting, puncture resistant lid, without sharps being able to come out
- upright and stable during use
- leak-resistant
- properly labeled to warn of hazardous waste inside the container

When your sharps disposal container is almost full, you will need to follow your community guidelines for the right way to dispose of your sharps disposal container. There may be state or local laws about how you should throw away used needles and syringes.

For more information about safe sharps disposal, and for specific information about sharps disposal in the state that you live in, go to the FDA's website at: www.fda.gov/safesharpsdisposal. You may also consult your pharmacist.

Need help?

Call your healthcare provider to talk about any questions you may have. For additional assistance or to share your feedback, call 800-526-7736.

Manufactured by:
Janssen Biotech, Inc.
Horsham, PA 19044, USA
US License No. 1864

This Instructions for Use has been approved by the U.S. Food and Drug Administration.

Approved: March / 2025

Instructions for Use

TREMFYA®
(trem fye' ah)
(guselkumab)

Prefilled Syringe

SINGLE-DOSE

Important

TREMFYA comes as a single-dose prefilled syringe containing one 100 mg dose. Each TREMFYA prefilled syringe can only be used one time. Throw the used prefilled syringe away (See Step 3) after one dose, even if there is medicine left in it. Do not reuse your TREMFYA prefilled syringe.

If your healthcare provider decides that you or a caregiver may be able to give your injections of TREMFYA at home, you should receive training on the right way to prepare and inject TREMFYA using the prefilled syringe before attempting to inject. Do not try to inject yourself until you have been shown the right way to give the injections by your healthcare provider.

For children, TREMFYA should be administered by a healthcare provider or an adult caregiver who has been shown the right way to give the injections by your healthcare provider.

Read this Instructions for Use before using your TREMFYA prefilled syringe and each time you get a refill. There may be new information. This leaflet does not take the place of talking with your healthcare provider about your medical condition or your treatment.

The TREMFYA prefilled syringe is intended for injection under the skin, not into the muscle or vein. After injection, the needle will retract into the body of the device and lock into place.

Storage information

Store in refrigerator at 36 °F to 46 °F (2 °C to 8 °C). Do not freeze TREMFYA prefilled syringe.

Keep TREMFYA prefilled syringe and all medicines out of reach of children.

Do not shake your TREMFYA prefilled syringe.

Keep TREMFYA prefilled syringe in the original carton to protect from light and physical damage.

Prefilled syringe parts

Before use

After use

You will need these supplies:

- 1 TREMFYA prefilled syringe

Not provided in the TREMFYA prefilled syringe carton:

- 1 Alcohol swab
- 1 Cotton ball or gauze pad
- 1 Adhesive bandage
- 1 Sharps container (See Step 3)

1. Prepare for your injection

Inspect carton

Remove your TREMFYA prefilled syringe carton from the refrigerator.

Keep the prefilled syringe in the carton and let it sit on a flat surface at room temperature for at least 30 minutes before use.

Do not warm the prefilled syringe any other way.

Check the expiration date ('EXP') on the back panel of the carton.

Do not use your prefilled syringe if the expiration date has passed.

Do not inject TREMFYA if the perforations on the carton are broken. Call your healthcare provider or pharmacist for a refill.

Choose injection site

Select from the following areas for your injection:

- Front of thighs (recommended)
- Lower stomach area (lower abdomen), except for a 2-inch area right around your navel (belly-button)
- Back of upper arms (only if someone else is giving you the injection)

Do not inject into skin that is tender, bruised, red, hard, thick, scaly or affected by psoriasis.

Clean injection site

Wash your hands well with soap and warm water.

Wipe your chosen injection site with an alcohol swab and allow it to dry.

Do not touch, fan, or blow on the injection site after you have cleaned it.

Inspect liquid

Take your TREMFYA prefilled syringe out of the carton.

Check the TREMFYA prefilled syringe liquid in the viewing window. It should be clear to slightly yellow and may contain tiny white or clear particles. You may also see one or more air bubbles. This is normal.

Do not inject if the liquid is cloudy or discolored, or has large particles. Call your healthcare provider or pharmacist for a refill.

2. Inject TREMFYA using prefilled syringe

Remove needle cover

Hold your prefilled syringe by the body and pull needle cover straight off. It is normal to see a drop of liquid.

Inject TREMFYA within 5 minutes of removing the needle cover.

Do not put needle cover back on, as this may damage the needle or cause a needle stick injury.

Do not touch needle or let it touch any surface.

Do not use a TREMFYA prefilled syringe if it is dropped. Call your healthcare provider or pharmacist for a refill.

Position fingers and insert needle

Place your thumb, index and middle fingers directly under the finger flange, as shown.

Do not touch plunger or area above finger flange as this may cause the needle safety device to activate.

Use your other hand to pinch skin at the injection site. Position syringe at about a 45 degree angle to the skin.

It is important to pinch enough skin to inject under the skin and not into the muscle.

Insert needle with a quick, dart-like motion.

Release pinch and reposition hand

Use your free hand to grasp the body of the prefilled syringe.

Press plunger

Place thumb from the opposite hand on the plunger and press the plunger all the way down until it stops.

Release pressure from plunger

The safety guard will cover the needle and lock into place, removing the needle from your skin.

3. After your injection

Dispose of your prefilled syringe

Put your used TREMFYA prefilled syringe in an FDA-cleared sharps disposal container right away after use.

Do not throw away (dispose of) your TREMFYA prefilled syringe in your household trash.

Do not recycle your used sharps disposal container.

For more information, see "How should I dispose of the used prefilled syringe?"

Check injection site

There may be a small amount of blood or liquid at the injection site. Hold pressure over your skin with a cotton ball or gauze pad until any bleeding stops.

Do not rub the injection site.

If needed, cover injection site with a bandage.

Need help?

Call your healthcare provider to talk about any questions you may have. For additional assistance or to share your feedback call 1-800-526-7736.

How should I dispose of the used prefilled syringe?

If you do not have an FDA-cleared sharps disposal container, you may use a household container that is:

- made of a heavy-duty plastic
- can be closed with a tight-fitting, puncture-resistant lid, without sharps being able to come out
- upright and stable during use
- leak-resistant
- properly labeled to warn of hazardous waste inside the container

When your sharps disposal container is almost full, you will need to follow your community guidelines for the right way to dispose of your sharps disposal container. There may be state or local laws about how you should throw away used needles and syringes.

For more information about safe sharps disposal, and for specific information about sharps disposal in the state that you live in, go to the FDA's website at: www.fda.gov/safesharpsdisposal

This Instructions for Use has been approved by the U.S. Food and Drug Administration.

Manufactured by:
Janssen Biotech, Inc.
Horsham, PA 19044, USA
U.S. License No. 1864

Approved: September 2025

INSTRUCTIONS FOR USE

TREMFYA®
[trem fye´ ah]
(guselkumab)
injection, for subcutaneous use
One-Press Patient-Controlled Injector

This "Instructions for Use" contains information on how to inject TREMFYA.

Important Information You Need to Know Before Injecting TREMFYA

TREMFYA comes in a single-dose One-Press injector containing one 100 mg dose.

During injection, push handle all the way down until teal body is not visible to inject the full dose.
DO NOT LIFT ONE-PRESS during injection. If you do, the One-Press will lock and you will not get the full dose.

Each One-Press injector can only be used one time. Throw away (See Step 3) after one dose, even if there is medicine left in it. Do not reuse your One-Press injector.

If your healthcare provider decides that you or a caregiver may be able to give your injections of TREMFYA at home, you should receive training on the right way to prepare and inject TREMFYA using the One-Press injector. Do not try to inject yourself until you have been trained by your healthcare provider.

For children, TREMFYA should be administered by a healthcare provider or an adult caregiver who has been shown the right way to give the injections by your healthcare provider.

Please read this Instructions for Use before using your One-Press injector and each time you get a new One-Press injector. There may be new information.

This leaflet does not take the place of talking with your healthcare provider about your medical condition or your treatment.

Storage information

Store in refrigerator at 36 °F to 46 °F (2 °C to 8 °C).

Do not freeze your One-Press injector.

Do not shake your One-Press injector.

Keep your One-Press injector and all medicines out of reach of children.

Keep your One-Press injector in the original carton to protect from light and physical damage.

Need help?

Call your healthcare provider to talk about any questions you may have. For additional assistance or to share your feedback call 1-800-526-7736.

One-Press injector parts

Before use After use

You will need:

- 1 One-Press injector

Not provided in the carton:

- 1 Alcohol swab
- 1 Cotton ball or gauze pad
- 1 Adhesive bandage
- 1 Sharps container (See Step 3)

1. Preparing to Inject TREMFYA

Inspect carton and allow TREMFYA to come to room temperature

Remove your One-Press injector carton from the refrigerator.

Keep your One-Press injector in the carton and let it sit on a flat surface at room temperature for at least 30 minutes before use.

Do not warm your One-Press injector any other way.

Check the expiration date ('EXP') on the carton

Do not use your One-Press injector if the expiration date has passed.

Do not inject TREMFYA if the seal on the carton is broken. Call your healthcare provider or pharmacist for a new One-Press injector.

Choose injection site

Select from the following areas for your injection:

- Front of thighs (recommended)
- Lower stomach area (lower abdomen), except for a 2-inch area right around your navel (belly-button)
- Back of upper arms (only for adults and only if someone else is giving you the injection). This injection site is not for use in children.

Do not inject into skin that is tender, bruised, red, hard, thick, scaly, or affected by psoriasis.

Wash hands

Wash your hands well with soap and warm water.

Clean injection site

Wipe your chosen injection site with an alcohol swab and allow it to dry.

Do not touch, fan, or blow on the injection site after you have cleaned it.

Inspect liquid in window

Take your One-Press injector out of the carton.

Check the liquid in the window. It should be clear to slightly yellow and may contain tiny white or clear particles. You may also see one or more air bubbles. This is normal.

Do not inject if the liquid is:

- cloudy,
- discolored, or
- has large particles.

Call your healthcare provider or pharmacist for a new One-Press injector.

2. Injecting TREMFYA

Pull off bottom cap

Keep hands away from the needle guard after the cap is removed. It is normal to see a few drops of liquid.

Inject TREMFYA within 5 minutes of removing the cap.

Do not put the cap back on. This could damage the needle.

Do not use a One-Press injector if it is dropped after removing the cap. Call your healthcare provider or pharmacist for a new One-Press injector.

Place straight on skin.

Push handle all the way down until teal body is not visible

DO NOT LIFT ONE-PRESS during injection!
If you do, the needle guard will lock, showing a yellow band, and you will not get the full dose.

You may hear a click when the injection begins. Keep pushing.

If you feel resistance, keep pushing. This is normal.

The medication injects as you push. Do this at a speed that is comfortable for you.

Confirm your injection is complete

Your injection is complete when:

- The teal body is not visible.
- You cannot press the handle down anymore.
- You may hear a click.

Lift straight up

The yellow band indicates that the needle guard is locked.

3. After your injection

Dispose of your One-Press injector

Put your used One-Press injector in a sharps disposal container right away after use.

Do not throw away (dispose of) your One-Press injector in your household trash.

Do not recycle your used sharps disposal container.

For more information, see "Disposing of TREMFYA One-Press injector".

Check injection site

There may be a small amount of blood or liquid at the injection site. Hold pressure over your skin with a cotton ball or gauze pad until any bleeding stops.

Do not rub the injection site.

If needed, cover injection site with a bandage.

Disposing of TREMFYA One-Press injector

If you do not have an FDA-cleared sharps disposal container, you may use a household container that is:

- made of a heavy-duty plastic
- can be closed with a tight-fitting, puncture-resistant lid, without sharps being able to come out
- upright and stable during use
- leak-resistant
- properly labeled to warn of hazardous waste inside the container

When your sharps disposal container is almost full, you will need to follow your community guidelines for the right way to dispose of your sharps disposal container. There may be state or local laws about how you should throw away used needles and syringes.

For more information about safe sharps disposal, and for specific information about sharps disposal in the state that you live in, go to the FDA's website at: www.fda.gov/safesharpsdisposal. You may also consult your pharmacist.

This Instructions for Use has been approved by the U.S. Food and Drug Administration.

Manufactured by:
Janssen Biotech, Inc.
Horsham, PA 19044, USA
U.S. License No. 1864

Revised: September 2025

INSTRUCTIONS FOR USE

TREMFYA® PEN
[trem fye' ah Pen]
(guselkumab)
injection, for subcutaneous use
100 mg/mL Prefilled Pen

This Instructions for Use contains information on how to inject with TREMFYA PEN.

SINGLE-DOSE

Important Information You Need to Know Before Injecting with TREMFYA PEN

TREMFYA PEN comes in a single-dose Prefilled Pen containing one 100 mg dose.

If your healthcare provider decides that you or a caregiver may be able to give your injections with TREMFYA PEN at home, you should receive training on the correct way to prepare and inject with TREMFYA PEN before using the Prefilled Pen.

For children, TREMFYA PEN should be administered by a healthcare provider or an adult caregiver who has been shown the right way to give the injections by your healthcare provider.

Read this Instructions for Use before using your Prefilled Pen and each time you get a new Prefilled Pen. There may be new information. This leaflet does not take the place of talking with your healthcare provider about your medical condition or your treatment.

Each TREMFYA PEN can only be used one time. Throw the used Prefilled Pen away (see Step 4) after one dose, even if there is still medicine left in it. Do not reuse your Prefilled Pen.

Store in refrigerator between 36 °F to 46 °F (2 °C to 8 °C).

Do not freeze your TREMFYA PEN.

Do not shake your TREMFYA PEN.

Keep your TREMFYA PEN and all medicines out of reach of children.

Keep your TREMFYA PEN in the original carton to protect from light and physical damage.

TREMFYA PEN parts

1. Get ready

Allow TREMFYA PEN to come to room temperature and inspect carton

Remove the carton from the refrigerator and let the carton sit on a flat surface at room temperature for approximately 30 minutes before use.

Do not warm the Prefilled Pen any other way.

Check to see that you have the correct medicine and dose.

Check the expiration ('EXP') date.

Do not use the Prefilled Pen if the expiration date has passed or if the seal on the carton is broken. Contact your healthcare provider or pharmacist for a new Prefilled Pen.

2. Prepare to inject with TREMFYA PEN

Take your Prefilled Pen out of the carton.

Inspect liquid in window to see that it is clear and colorless to slightly yellow

Check the liquid in the viewing window. It should be clear and colorless to slightly yellow and may contain tiny white or clear particles. You may also see air bubbles. This is normal.

Do not inject if the liquid is:

- cloudy or
- discolored or
- has large particles

Call your healthcare provider or pharmacist for a new Prefilled Pen.

Choose injection site

Select from the following areas for your injection:

- Front of thighs
- Lower stomach area (lower abdomen), except for a 2-inch area right around your navel (belly-button)
- Back of upper arms (only for adults and only if someone else is giving you the injection). This injection site is not for use in children.

Do not inject into skin that is tender, bruised, red, scaly, thick or hard. Avoid areas with scars or stretch marks.

Wash hands and clean injection site

Wash your hands well with soap and warm water.

Wipe your chosen injection site with an alcohol swab and allow it to dry.

Do not touch, fan, or blow on the injection site after you have cleaned it.

3. Inject with TREMFYA PEN

Remove cap when you are ready to inject

Do Not Touch Teal Needle Guard!
This may start the injection and you will not receive the dose.

Pull the cap straight off. It is normal to see a few drops of liquid.

Inject with TREMFYA PEN within 5 minutes of removing cap.

Do not put the cap back on as this may damage the needle.

Do not use your Prefilled Pen if it is dropped after removing the cap. Call your healthcare provider or pharmacist for a new Prefilled Pen.

Position the Prefilled Pen straight onto the injection site then push and hold the Prefilled Pen

Do Not Lift The Prefilled Pen During Injection!
If you do, the teal needle guard will lock and the full dose will not be delivered.

Position your Prefilled Pen straight onto the injection site with the teal needle guard against the skin and the viewing window facing you.

Press down on the Prefilled Pen and keep holding it down against the skin.

You will hear the first click.

Keep holding your Prefilled Pen firmly against the skin for about 10 seconds to hear a second click

You are almost done.

Keep holding firmly against the skin and confirm your injection is complete

Your injection is complete when the yellow plunger rod stops moving and fills the viewing window.

Lift straight up

4. After your injection

Check injection site

There may be a small amount of blood or liquid at the injection site. Gently hold pressure over the injection site with a cotton ball or gauze pad until any bleeding stops.

Do not rub the injection site. If needed, cover the injection site with a bandage.

Dispose of your Prefilled Pen and cap

Put your used Prefilled Pen and cap in an FDA-cleared sharps disposal container right away after use.

Do not throw away (dispose of) your Prefilled Pen in your household trash.

Do not recycle your used sharps disposal container.

For more information, see Disposing of TREMFYA PEN.

Disposing of TREMFYA PEN

If you do not have an FDA-cleared sharps disposal container, you may use a household container that is:

- made of heavy-duty plastic
- can be closed with a tight-fitting, puncture resistant lid, without sharps being able to come out
- upright and stable during use
- leak-resistant
- properly labeled to warn of hazardous waste inside the container

When your sharps disposal container is almost full, you will need to follow your community guidelines for the right way to dispose of your sharps disposal container. There may be state or local laws about how you should throw away used needles and syringes.

For more information about safe sharps disposal, and for specific information about sharps disposal in the state that you live in, go to the FDA's website at: www.fda.gov/safesharpsdisposal. You may also consult your pharmacist.

Call your healthcare provider to talk about any questions you may have. For additional assistance or to share your feedback, call 1-800-526-7736.

Manufactured by:
Janssen Biotech, Inc.
Horsham, PA 19044, USA
U.S. License No. 1864

This Instructions for Use has been approved by the U.S. Food and Drug Administration.

Approved: September / 2025

PRINCIPAL DISPLAY PANEL - 100 mg/mL Syringe Carton - NDC 57894-640-01

Tremfya®
(guselkumab)
Injection

100 mg/mL

FOR SUBCUTANEOUS USE ONLY

Rx only

NDC 57894-640-01

One single-dose prefilled syringe
Discard unused portion
Contains no preservative

ATTENTION: Dispense the enclosed
Medication Guide to each patient

PRINCIPAL DISPLAY PANEL - 100 mg/mL Syringe Carton - NDC 57894-640-11

Tremfya®
(guselkumab)
Injection

100 mg/mL

FOR SUBCUTANEOUS USE ONLY
Rx only

NDC 57894-640-11

Single-dose One-Press
patient-controlled injector

Discard unused portion
Contains no preservative

ATTENTION: Dispense the enclosed
Medication Guide to each patient

PRINCIPAL DISPLAY PANEL - 100 mg/mL Pen Carton

NDC 57894-640-06

Tremfya® PEN
(guselkumab)
Injection

100 mg/mL

FOR SUBCUTANEOUS USE ONLY

Rx only

One single-dose prefilled pen
Discard unused portion

Attention: Dispense the enclosed
Medication Guide to each patient.

PRINCIPAL DISPLAY PANEL - 200 mg/20 mL Vial Carton

NDC 57894-650-02

Tremfya®
(guselkumab)
Injection

200 mg/20 mL
(10 mg/mL)

FOR INTRAVENOUS
INFUSION ONLY

Attention: Dispense the
enclosed Medication Guide
to each patient.
Rx only

Single-dose vial
Discard unused portion

PRINCIPAL DISPLAY PANEL - 200 mg/2 mL Pen Carton

NDC 57894-651-02

Tremfya® PEN
(guselkumab)
Injection

200 mg/2 mL

FOR SUBCUTANEOUS USE ONLY

Rx only

One single-dose prefilled pen
Discard unused portion

ATTENTION: Dispense the enclosed
Medication Guide to each patient.

PRINCIPAL DISPLAY PANEL - 200 mg/2 mL Syringe Carton

NDC 57894-651-22

Tremfya®
(guselkumab)
Injection

200 mg/2 mL

FOR SUBCUTANEOUS USE ONLY

Rx only

One single-dose prefilled syringe
Discard unused portion

ATTENTION: Dispense the enclosed
Medication Guide to each patient.

PRINCIPAL DISPLAY PANEL - 200 mg/2 mL Pen Carton - NDC 57894-651-04

NDC 57894-651-04
Rx only

Tremfya® PEN
(guselkumab)
Injection

200 mg/2 mL

FOR SUBCUTANEOUS USE ONLY

Induction Pack for Crohn's Disease
and Ulcerative Colitis
(includes 1 induction dose)

The entire carton is to
be dispensed as a unit.

Contains: Two cartons each containing
one single-dose prefilled pen.
Discard unused portion.

ATTENTION: Dispense the enclosed
Medication Guide to each patient.